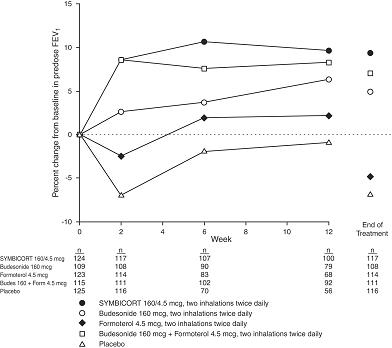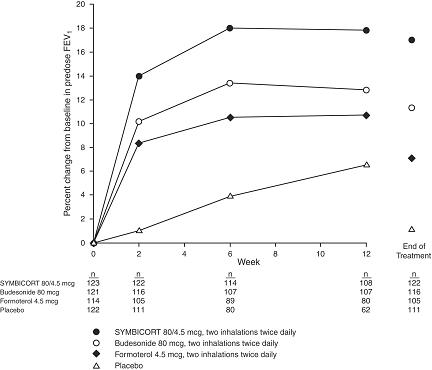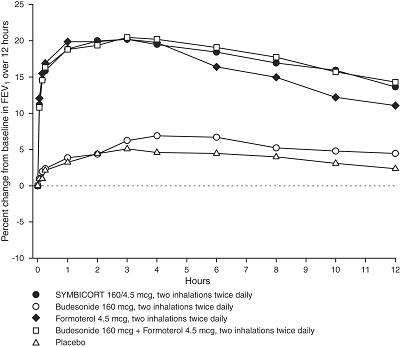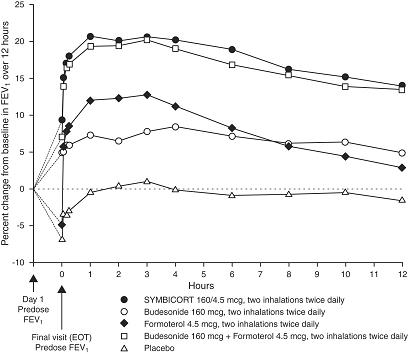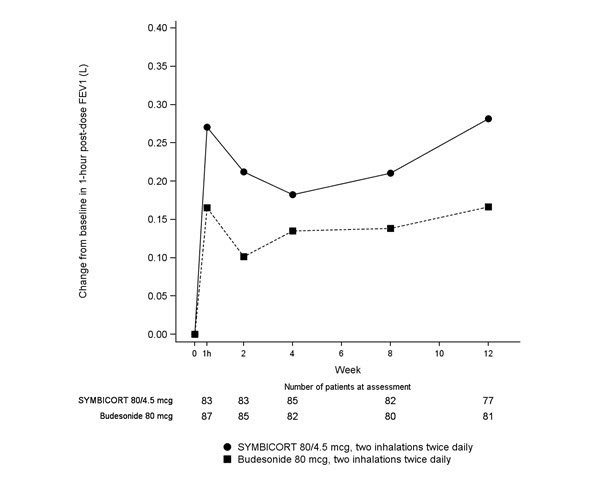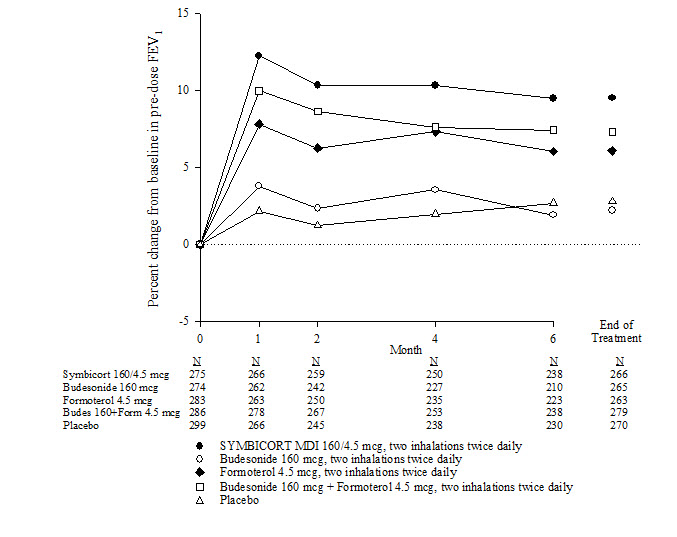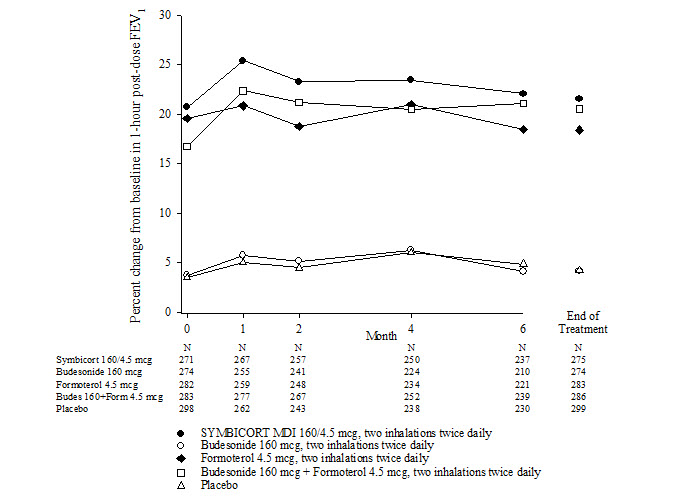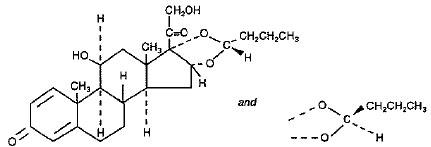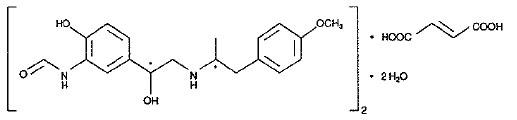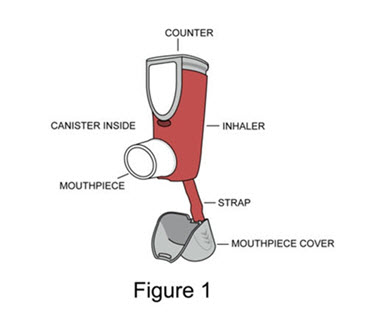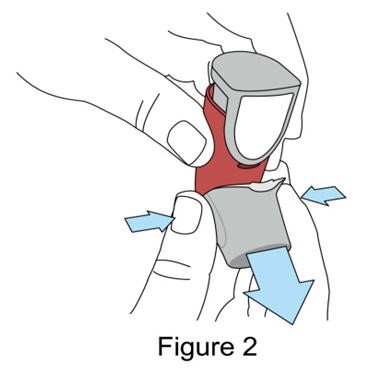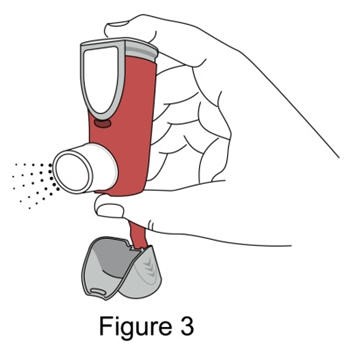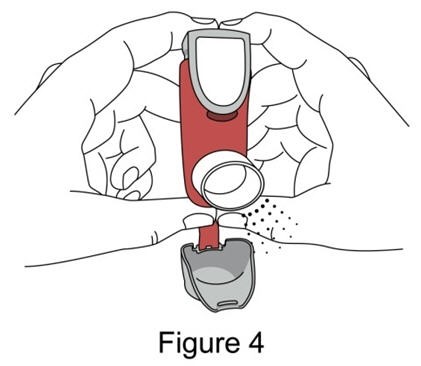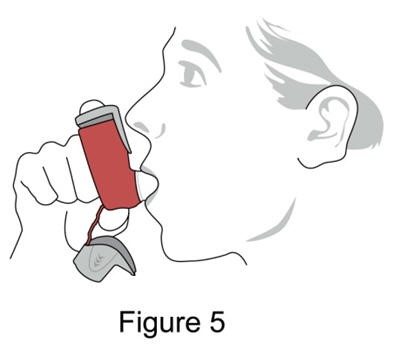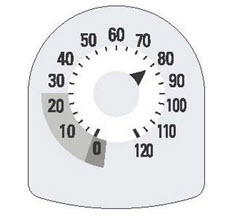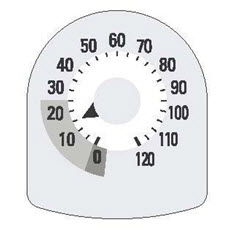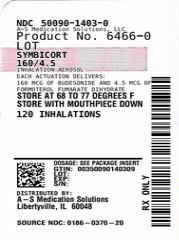 DRUG LABEL: SYMBICORT
NDC: 50090-1403 | Form: AEROSOL
Manufacturer: A-S Medication Solutions
Category: prescription | Type: HUMAN PRESCRIPTION DRUG LABEL
Date: 20241022

ACTIVE INGREDIENTS: BUDESONIDE 160 ug/1 1; FORMOTEROL FUMARATE 4.5 ug/1 1
INACTIVE INGREDIENTS: HYDROFLUOROCARBON 227EA; POLYETHYLENE GLYCOL 1000; POVIDONE K25

HIGHLIGHTS OF PRESCRIBING INFORMATION

These highlights do not include all the information needed to use SYMBICORT safely and effectively. See full prescribing information for SYMBICORT.
SYMBICORT® (budesonide and formoterol fumarate dihydrate) Inhalation Aerosol, for oral inhalation use
Initial U.S. Approval: 2006

1 INDICATIONS AND USAGE

SYMBICORT is a combination product containing a corticosteroid and a long-acting beta2-adrenergic agonist indicated for:

- Treatment of asthma in patients 6 years of age and older. (1.1)
- Maintenance treatment of airflow obstruction and reducing exacerbations in patients with chronic obstructive pulmonary disease (COPD) including chronic bronchitis and/or emphysema. (1.2)

Important limitations:

- Not indicated for the relief of acute bronchospasm. (1.1, 1.2)

2 DOSAGE AND ADMINISTRATION

For oral inhalation only.

- Treatment of asthma in patients 12 years and older: 2 inhalations of SYMBICORT 80/4.5 or 160/4.5 twice daily. Starting dosage is based on asthma severity. (2.2)
- Treatment of asthma in patients aged 6 to less than 12 years: 2 inhalations of SYMBICORT 80/4.5 twice daily. (2.2)
- Maintenance treatment in COPD: 2 inhalations of SYMBICORT 160/4.5 twice daily. (2.3)

3 DOSAGE FORMS AND STRENGTHS

Metered-dose inhaler containing a combination of budesonide (80 or 160 mcg) and formoterol (4.5 mcg) as an inhalation aerosol. (3)

4 CONTRAINDICATIONS

- Primary treatment of status asthmaticus or acute episodes of asthma or COPD requiring intensive measures. (4)
- Hypersensitivity to any of the ingredients in SYMBICORT. (4)

5 WARNINGS AND PRECAUTIONS

- Serious asthma-related events: Long-acting beta2-adrenergic agonists as monotherapy increase the risk. (5.1)
- Deterioration of disease and acute episodes: Do not initiate in acutely deteriorating asthma or COPD or to treat acute symptoms. (5.2)
- Use with additional long-acting beta2-agonist: Do not use in combination because of risk of overdose. (5.3)
- Localized infections: Candida albicans infection of the mouth and throat may occur. Monitor patients periodically for signs of adverse effects on the oral cavity. Advise the patient to rinse his/her mouth with water without swallowing after inhalation to help reduce the risk. (5.4)
- Pneumonia: Increased risk in patients with COPD. Monitor patients for signs and symptoms of pneumonia and other potential lung infections. (5.5)
- Immunosuppression: Potential worsening of infections (e.g., existing tuberculosis, fungal, bacterial, viral, or parasitic infection; or ocular herpes simplex). Use with caution in patients with these infections. More serious or even fatal course of chickenpox or measles can occur in susceptible patients. (5.6)
- Transferring patients from systemic corticosteroids: Risk of impaired adrenal function when transferring from oral steroids. Taper patients slowly from systemic corticosteroids if transferring to SYMBICORT. (5.7)
- Hypercorticism and adrenal suppression: May occur with very high dosages or at the regular dosage in susceptible individuals. If such changes occur, discontinue SYMBICORT slowly. (5.8)
- Strong cytochrome P450 3A4 inhibitors (e.g., ritonavir): Risk of increased systemic corticosteroid effects. Exercise caution when used with SYMBICORT. (5.9)
- Paradoxical bronchospasm: Discontinue SYMBICORT and institute alternative therapy if paradoxical bronchospasm occurs. (5.10)
- Patients with cardiovascular or central nervous system disorders: Use with caution because of beta-adrenergic stimulation. (5.12)
- Decreases in bone mineral density: Assess bone mineral density initially and periodically thereafter. (5.13)
- Effects on growth: Monitor growth of pediatric patients. (5.14)
- Glaucoma and cataracts: Close monitoring is warranted. (5.15)
- Metabolic effects: Be alert to eosinophilic conditions, hypokalemia, and hyperglycemia. (5.16, 5.18)
- Coexisting conditions: Use with caution in patients with convulsive disorders, thyrotoxicosis, diabetes mellitus, and ketoacidosis. (5.17)

6 ADVERSE REACTIONS

Most common adverse reactions (incidence >3%) are:

- Asthma: nasopharyngitis, headache, upper respiratory tract infection, pharyngolaryngeal pain, sinusitis, influenza, back pain, nasal congestion, stomach discomfort, vomiting, and oral candidiasis. (6.1)
- COPD: nasopharyngitis, oral candidiasis, bronchitis, sinusitis, upper respiratory tract infections. (6.2)

To report SUSPECTED ADVERSE REACTIONS, contact AstraZeneca at 1-800-236-9933 or FDA at 1-800-FDA-1088 or www.fda.gov/medwatch.

7 DRUG INTERACTIONS

- Strong cytochrome P450 3A4 inhibitors (e.g., ritonavir): Use with caution. May cause increased systemic corticosteroid effects. (7.1)
- Monoamine oxidase inhibitors and tricyclic antidepressants: Use with extreme caution. May potentiate effect of formoterol on vascular system. (7.2)
- Beta-blockers: Use with caution. May block bronchodilatory effects of beta-agonists and produce severe bronchospasm. (7.3)
- Diuretics: Use with caution. Electrocardiographic changes and/or hypokalemia associated with non-potassium-sparing diuretics may worsen with concomitant beta-agonists. (7.4)

8 USE IN SPECIFIC POPULATIONS

Hepatic impairment: Monitor patients for signs of increased drug exposure. (8.6)

FULL PRESCRIBING INFORMATION

1 INDICATIONS AND USAGE

1.1 Treatment of Asthma

SYMBICORT is indicated for the treatment of asthma in patients 6 years of age and older.

SYMBICORT should be used for patients not adequately controlled on a long-term asthma-control medication such as an inhaled corticosteroid (ICS) or whose disease warrants initiation of treatment with both an inhaled corticosteroid and long-acting beta2-adrenergic agonist (LABA).

Important Limitations of Use:

- SYMBICORT is NOT indicated for the relief of acute bronchospasm.

1.2 Maintenance Treatment of Chronic Obstructive Pulmonary Disease

SYMBICORT 160/4.5 is indicated for the maintenance treatment of airflow obstruction in patients with chronic obstructive pulmonary disease (COPD) including chronic bronchitis and/or emphysema. SYMBICORT 160/4.5 is also indicated to reduce exacerbations of COPD. SYMBICORT 160/4.5 is the only strength indicated for the treatment of COPD.

Important Limitations of Use:

- SYMBICORT is NOT indicated for the relief of acute bronchospasm.

2 DOSAGE AND ADMINISTRATION

2.1 Administration Information

SYMBICORT should be administered as 2 inhalations twice daily (morning and evening, approximately 12 hours apart), every day by the orally inhaled route only. After inhalation, the patient should rinse the mouth with water without swallowing.

Prime SYMBICORT before using for the first time by releasing two test sprays into the air away from the face, shaking well for 5 seconds before each spray. In cases where the inhaler has not been used for more than 7 days or when it has been dropped, prime the inhaler again by shaking well before each spray and releasing two test sprays into the air away from the face.

More frequent administration or a higher number of inhalations (more than 2 inhalations twice daily) of the prescribed strength of SYMBICORT is not recommended as some patients are more likely to experience adverse effects with higher doses of formoterol. Patients using SYMBICORT should not use additional LABA for any reason [see Warnings and Precautions (5.3, 5.12)].

2.2 Asthma

If asthma symptoms arise in the period between doses, an inhaled, short-acting beta2-agonist should be taken for immediate relief.

Adult and Adolescent Patients 12 Years of Age and Older

For patients 12 years of age and older, the dosage is 2 inhalations of SYMBICORT 80/4.5 or SYMBICORT 160/4.5 twice daily.

The recommended starting dosages for SYMBICORT for patients 12 years of age and older are based upon patients' asthma severity or level of control of asthma symptoms, and risk of exacerbations on current inhaled corticosteroids.

The maximum recommended dosage in adult and adolescent patients 12 years and older is SYMBICORT 160/4.5, two inhalations twice daily.

Improvement in asthma control following inhaled administration of SYMBICORT can occur within 15 minutes of beginning treatment, although maximum benefit may not be achieved for 2 weeks or longer after beginning treatment. Individual patients will experience a variable time to onset and degree of symptom relief.

For patients who do not respond adequately to the starting dose after 1-2 weeks of therapy with SYMBICORT 80/4.5, replacement with SYMBICORT 160/4.5 may provide additional asthma control.

If a previously effective dosage regimen of SYMBICORT fails to provide adequate control of asthma, the therapeutic regimen should be re-evaluated and additional therapeutic options, (e.g., replacing the lower strength of SYMBICORT with the higher strength, adding additional inhaled corticosteroid, or initiating oral corticosteroids) should be considered.

Pediatric Patients Aged 6 to Less than 12 Years

For patients 6 to less than 12 years of age, the dosage is 2 inhalations of SYMBICORT 80/4.5 twice daily.

2.3 Chronic Obstructive Pulmonary Disease

For patients with COPD the recommended dose is SYMBICORT 160/4.5, two inhalations twice daily.

If shortness of breath occurs in the period between doses, an inhaled, short-acting beta2-agonist should be taken for immediate relief.

3 DOSAGE FORMS AND STRENGTHS

SYMBICORT is available as a metered-dose inhaler containing a combination of budesonide (80 or 160 mcg) and formoterol (4.5 mcg) as an inhalation aerosol in the following two strengths: 80/4.5 and 160/4.5. Each dosage strength contains 60 or 120 actuations per/canister. Each strength of SYMBICORT is supplied with a red plastic actuator with a gray dust cap.

4 CONTRAINDICATIONS

The use of SYMBICORT is contraindicated in the following conditions:

- Primary treatment of status asthmaticus or other acute episodes of asthma or COPD where intensive measures are required.
- Hypersensitivity to any of the ingredients in SYMBICORT.

5 WARNINGS AND PRECAUTIONS

5.1 Serious Asthma-Related Events – Hospitalizations, Intubations and Death

Use of LABA as monotherapy (without ICS) for asthma is associated with an increased risk of asthma-related death [see Salmeterol Multicenter Asthma Research Trial (SMART)]. Available data from controlled clinical trials also suggest that use of LABA as monotherapy increases the risk of asthma-related hospitalization in pediatric and adolescent patients. These findings are considered a class effect of LABA. When LABA are used in fixed-dose combination with ICS, data from large clinical trials do not show a significant increase in the risk of serious asthma-related events (hospitalizations, intubations, death) compared to ICS alone (see Serious Asthma-Related Events with ICS/LABA).

Serious Asthma-Related Events with ICS/LABA

Four large, 26-week, randomized, blinded, active-controlled clinical safety trials were conducted to evaluate the risk of serious asthma-related events when LABA were used in fixed-dose combination with ICS compared to ICS alone in patients with asthma. Three trials included adult and adolescent patients aged ≥12 years: one trial compared budesonide/formoterol (SYMBICORT) to budesonide [see Clinical Studies (14.1)]; one trial compared fluticasone propionate/salmeterol inhalation powder to fluticasone propionate inhalation powder; and one trial compared mometasone furoate/formoterol to mometasone furoate. The fourth trial included pediatric patients 4 to 11 years of age and compared fluticasone propionate/salmeterol inhalation powder to fluticasone propionate inhalation powder. The primary safety endpoint for all four trials was serious asthma-related events (hospitalizations, intubations and death). A blinded adjudication committee determined whether events were asthma-related.

The three adult and adolescent trials were designed to rule out a risk margin of 2.0, and the pediatric trial was designed to rule out a risk of 2.7. Each individual trial met its pre-specified objective and demonstrated non-inferiority of ICS/LABA to ICS alone. A meta-analysis of the three adult and adolescent trials did not show a significant increase in risk of a serious asthma-related event with ICS/LABA fixed-dose combination compared with ICS alone (Table 1). These trials were not designed to rule out all risk for serious asthma-related events with ICS/LABA compared with ICS.

Table 1. Meta-analysis of Serious Asthma-Related Events in Patients with Asthma Aged 12 Years and Older
 | ICS/LABA; (N = 17,537) [Randomized patients who had taken at least 1 dose of study drug. Planned treatment used for analysis.] | ICS; (N = 17,552) | ICS/LABA vs ICS; Hazard ratio (95% CI) [Estimated using a Cox proportional hazards model of time to first event with baseline hazards stratified by each of the 3 trials.]
Serious asthma-related event [Number of patients with event that occurred within 6 months after the first use of study drug or 7 days after the last date of study drug, whichever date was later. Patients can have one or more events, but only the first event was counted for analysis. A single, blinded, independent adjudication committee determined whether events were asthma-related.] | 116 | 105 | 1.10 (0.85, 1.44)
Asthma-related death | 2 | 0
Asthma-related intubation (endotracheal) | 1 | 2
Asthma-related hospitalization (≥24-hour stay) | 115 | 105
ICS = Inhaled Corticosteroid, LABA = Long-acting Beta2-adrenergic Agonist

The pediatric safety trial included 6208 pediatric patients 4 to 11 years of age who received ICS/LABA (fluticasone propionate /salmeterol inhalation powder) or ICS (fluticasone propionate inhalation powder). In this trial, 27/3107 (0.9%) patients randomized to ICS/LABA and 21/3101 (0.7%) patients randomized to ICS experienced a serious asthma-related event. There were no asthma-related deaths or intubations. ICS/LABA did not show a significantly increased risk of a serious asthma-related event compared to ICS based on the pre-specified risk margin (2.7), with an estimated hazard ratio of time to first event of 1.29 (95% CI: 0.73, 2.27).

Salmeterol Multicenter Asthma Research Trial (SMART)

A 28-week, placebo-controlled U.S. trial that compared the safety of salmeterol with placebo, each added to usual asthma therapy, showed an increase in asthma-related deaths in patients receiving salmeterol (13/13,176 in patients treated with salmeterol vs. 3/13,179 in patients treated with placebo; relative risk: 4.37 [95% CI 1.25, 15.34]). Use of background ICS was not required in SMART. The increased risk of asthma-related death is considered a class effect of LABA monotherapy.

Formoterol Monotherapy Studies

Clinical studies with formoterol used as monotherapy suggested a higher incidence of serious asthma exacerbation in patients who received formoterol than in those who received placebo. The sizes of these studies were not adequate to precisely quantify the difference in serious asthma exacerbations between treatment groups.

5.2 Deterioration of Disease and Acute Episodes

SYMBICORT should not be initiated in patients during rapidly deteriorating or potentially life-threatening episodes of asthma or COPD. SYMBICORT has not been studied in patients with acutely deteriorating asthma or COPD. The initiation of SYMBICORT in this setting is not appropriate.

Increasing use of inhaled, short-acting beta2-agonists is a marker of deteriorating asthma. In this situation, the patient requires immediate re-evaluation with reassessment of the treatment regimen, giving special consideration to the possible need for replacing the current strength of SYMBICORT with a higher strength, adding additional inhaled corticosteroid, or initiating systemic corticosteroids. Patients should not use more than 2 inhalations twice daily (morning and evening) of SYMBICORT.

SYMBICORT should not be used for the relief of acute symptoms, i.e., as rescue therapy for the treatment of acute episodes of bronchospasm. An inhaled, short-acting beta2-agonist, not SYMBICORT, should be used to relieve acute symptoms such as shortness of breath.

When beginning treatment with SYMBICORT, patients who have been taking oral or inhaled, short-acting beta2-agonists on a regular basis (e.g., 4 times a day) should be instructed to discontinue the regular use of these drugs.

5.3 Excessive Use of SYMBICORT and Use with Other Long-Acting Beta2-Agonists

As with other inhaled drugs containing beta2-adrenergic agents, SYMBICORT should not be used more often than recommended, at higher doses than recommended, or in conjunction with other medications containing LABA, as an overdose may result. Clinically significant cardiovascular effects and fatalities have been reported in association with excessive use of inhaled sympathomimetic drugs. Patients using SYMBICORT should not use an additional LABA (e.g., salmeterol, formoterol fumarate, arformoterol tartrate) for any reason, including prevention of exercise-induced bronchospasm (EIB) or the treatment of asthma or COPD.

5.4 Local Effects

In clinical studies, the development of localized infections of the mouth and pharynx with Candida albicans has occurred in patients treated with SYMBICORT. When such an infection develops, it should be treated with appropriate local or systemic (i.e., oral antifungal) therapy while treatment with SYMBICORT continues, but at times therapy with SYMBICORT may need to be interrupted. Advise the patient to rinse his/her mouth with water without swallowing following inhalation to help reduce the risk of oropharyngeal candidiasis.

5.5 Pneumonia and Other Lower Respiratory Tract Infections

Physicians should remain vigilant for the possible development of pneumonia in patients with COPD as the clinical features of pneumonia and exacerbations frequently overlap. Lower respiratory tract infections, including pneumonia, have been reported following the inhaled administration of corticosteroids.

In a 6-month lung function study of 1704 patients with COPD, there was a higher incidence of lung infections other than pneumonia (e.g., bronchitis, viral lower respiratory tract infections, etc.) in patients receiving SYMBICORT 160/4.5 (7.6%) than in those receiving SYMBICORT 80/4.5 (3.2%), formotero1 4.5 mcg (4.6%) or placebo (3.3%). Pneumonia did not occur with greater incidence in the SYMBICORT 160/4.5 group (1.1 %) compared with placebo (1.3%). In a 12-month lung function study of 1964 patients with COPD, there was also a higher incidence of lung infections other than pneumonia in patients receiving SYMBICORT 160/4.5 (8.1%) than in those receiving SYMBICORT 80/4.5 (6.9%), formoterol 4.5 mcg (7.1%) or placebo (6.2%). Similar to the 6-month study, pneumonia did not occur with greater incidence in the SYMBICORT 160/4.5 group (4.0%) compared with placebo (5.0%).

5.6 Immunosuppression

Patients who are on drugs that suppress the immune system are more susceptible to infection than healthy individuals. Chicken pox and measles, for example, can have a more serious or even fatal course in susceptible children or adults using corticosteroids. In such children or adults who have not had these diseases or been properly immunized, particular care should be taken to avoid exposure. How the dose, route, and duration of corticosteroid administration affects the risk of developing a disseminated infection is not known. The contribution of the underlying disease and/or prior corticosteroid treatment to the risk is also not known. If exposed, therapy with varicella zoster immune globulin (VZIG) or pooled intravenous immunoglobulin (IVIG), as appropriate, may be indicated. If exposed to measles, prophylaxis with pooled intramuscular immunoglobulin (IG) may be indicated (see the respective package inserts for complete VZIG and IG prescribing information). If chicken pox develops, treatment with antiviral agents may be considered. The immune responsiveness to varicella vaccine was evaluated in pediatric patients with asthma ages 12 months to 8 years with budesonide inhalation suspension.

An open-label, nonrandomized clinical study examined the immune responsiveness to varicella vaccine in 243 asthma patients 12 months to 8 years of age who were treated with budesonide inhalation suspension 0.25 mg to 1 mg daily (n=151) or noncorticosteroid asthma therapy (n=92) (i.e., beta2-agonists, leukotriene receptor antagonists, cromones). The percentage of patients developing a seroprotective antibody titer of >5.0 (gpELISA value) in response to the vaccination was similar in patients treated with budesonide inhalation suspension (85%), compared to patients treated with noncorticosteroid asthma therapy (90%). No patient treated with budesonide inhalation suspension developed chicken pox as a result of vaccination.

Inhaled corticosteroids should be used with caution, if at all, in patients with active or quiescent tuberculosis infections of the respiratory tract; untreated systemic fungal, bacterial, viral, or parasitic infections; or ocular herpes simplex.

5.7 Transferring Patients From Systemic Corticosteroid Therapy

Particular care is needed for patients who have been transferred from systemically active corticosteroids to inhaled corticosteroids because deaths due to adrenal insufficiency have occurred in patients with asthma during and after transfer from systemic corticosteroids to less systemically available inhaled corticosteroids. After withdrawal from systemic corticosteroids, a number of months are required for recovery of hypothalamic-pituitary-adrenal (HPA) function.

Patients who have been previously maintained on 20 mg or more per day of prednisone (or its equivalent) may be most susceptible, particularly when their systemic corticosteroids have been almost completely withdrawn. During this period of HPA suppression, patients may exhibit signs and symptoms of adrenal insufficiency when exposed to trauma, surgery, or infection (particularly gastroenteritis) or other conditions associated with severe electrolyte loss. Although SYMBICORT may provide control of asthma symptoms during these episodes, in recommended doses it supplies less than normal physiological amounts of glucocorticoid systemically and does NOT provide the mineralocorticoid activity that is necessary for coping with these emergencies.

During periods of stress, a severe asthma attack or a severe COPD exacerbation, patients who have been withdrawn from systemic corticosteroids should be instructed to resume oral corticosteroids (in large doses) immediately and to contact their physicians for further instruction. These patients should also be instructed to carry a warning card indicating that they may need supplementary systemic corticosteroids during periods of stress, a severe asthma attack, or a severe COPD exacerbation.

Patients requiring oral corticosteroids should be weaned slowly from systemic corticosteroid use after transferring to SYMBICORT. Prednisone reduction can be accomplished by reducing the daily prednisone dose by 2.5 mg on a weekly basis during therapy with SYMBICORT. Lung function (mean forced expiratory volume in 1 second [FEV1] or morning peak expiratory flow [PEF]), beta-agonist use, and asthma or COPD symptoms should be carefully monitored during withdrawal of oral corticosteroids. In addition, patients should be observed for signs and symptoms of adrenal insufficiency, such as fatigue, lassitude, weakness, nausea and vomiting, and hypotension.

Transfer of patients from systemic corticosteroid therapy to inhaled corticosteroids or SYMBICORT may unmask conditions previously suppressed by the systemic corticosteroid therapy (e.g., rhinitis, conjunctivitis, eczema, arthritis, eosinophilic conditions). Some patients may experience symptoms of systemically active corticosteroid withdrawal (e.g., joint and/or muscular pain, lassitude, depression) despite maintenance or even improvement of respiratory function.

5.8 Hypercorticism and Adrenal Suppression

Budesonide, a component of SYMBICORT, will often help control asthma and COPD symptoms with less suppression of HPA function than therapeutically equivalent oral doses of prednisone. Since budesonide is absorbed into the circulation and can be systemically active at higher doses, the beneficial effects of SYMBICORT in minimizing HPA dysfunction may be expected only when recommended dosages are not exceeded and individual patients are titrated to the lowest effective dose.

Because of the possibility of systemic absorption of inhaled corticosteroids, patients treated with SYMBICORT should be observed carefully for any evidence of systemic corticosteroid effects. Particular care should be taken in observing patients postoperatively or during periods of stress for evidence of inadequate adrenal response.

It is possible that systemic corticosteroid effects such as hypercorticism and adrenal suppression (including adrenal crisis) may appear in a small number of patients, particularly when budesonide is administered at higher than recommended doses over prolonged periods of time. If such effects occur, the dosage of SYMBICORT should be reduced slowly, consistent with accepted procedures for reducing systemic corticosteroids and for management of asthma symptoms.

5.9 Drug Interactions With Strong Cytochrome P450 3A4 Inhibitors

Caution should be exercised when considering the coadministration of SYMBICORT with ketoconazole, and other known strong CYP3A4 inhibitors (e.g., ritonavir, atazanavir, clarithromycin, indinavir, itraconazole, nefazodone, nelfinavir, saquinavir, telithromycin) because adverse effects related to increased systemic exposure to budesonide may occur [see Drug Interactions (7.1) and Clinical Pharmacology (12.3)].

5.10 Paradoxical Bronchospasm and Upper Airway Symptoms

As with other inhaled medications, SYMBICORT can produce paradoxical bronchospasm, which may be life threatening. If paradoxical bronchospasm occurs following dosing with SYMBICORT, it should be treated immediately with an inhaled, short-acting bronchodilator, SYMBICORT should be discontinued immediately, and alternative therapy should be instituted.

5.11 Immediate Hypersensitivity Reactions

Immediate hypersensitivity reactions may occur after administration of SYMBICORT, as demonstrated by cases of urticaria, angioedema, rash, and bronchospasm.

5.12 Cardiovascular and Central Nervous System Effects

Excessive beta-adrenergic stimulation has been associated with seizures, angina, hypertension or hypotension, tachycardia with rates up to 200 beats/min, arrhythmias, nervousness, headache, tremor, palpitation, nausea, dizziness, fatigue, malaise, and insomnia [see Overdosage (10)]. Therefore, SYMBICORT, like all products containing sympathomimetic amines, should be used with caution in patients with cardiovascular disorders, especially coronary insufficiency, cardiac arrhythmias, and hypertension.

Formoterol, a component of SYMBICORT, can produce a clinically significant cardiovascular effect in some patients as measured by pulse rate, blood pressure, and/or symptoms. Although such effects are uncommon after administration of formoterol at recommended doses, if they occur, the drug may need to be discontinued. In addition, beta-agonists have been reported to produce ECG changes, such as flattening of the T wave, prolongation of the QTc interval, and ST segment depression. The clinical significance of these findings is unknown. Fatalities have been reported in association with excessive use of inhaled sympathomimetic drugs.

5.13 Reduction in Bone Mineral Density

Decreases in bone mineral density (BMD) have been observed with long-term administration of products containing inhaled corticosteroids. The clinical significance of small changes in BMD with regard to long-term consequences such as fracture is unknown. Patients with major risk factors for decreased bone mineral content, such as prolonged immobilization, family history of osteoporosis, postmenopausal status, tobacco use, advanced age, poor nutrition, or chronic use of drugs that can reduce bone mass (e.g., anticonvulsants, oral corticosteroids) should be monitored and treated with established standards of care. Since patients with COPD often have multiple risk factors for reduced BMD, assessment of BMD is recommended prior to initiating SYMBICORT and periodically thereafter. If significant reductions in BMD are seen and SYMBICORT is still considered medically important for that patient's COPD therapy, use of medication to treat or prevent osteoporosis should be strongly considered.

Effects of treatment with SYMBICORT 160/4.5, SYMBICORT 80/4.5, formoterol 4.5 mcg, or placebo on BMD was evaluated in a subset of 326 patients (females and males 41 to 88 years of age) with COPD in the 12-month lung function study. BMD evaluations of the hip and lumbar spine regions were conducted at baseline and 52 weeks using dual energy x-ray absorptiometry (DEXA) scans. Mean changes in BMD from baseline to end of treatment were small (mean changes ranged from -0.01 - 0.01 g/cm^2). ANCOVA results for total spine and total hip BMD based on the end of treatment time point showed that all geometric LS Mean ratios for the pairwise treatment group comparisons were close to 1, indicating that overall, BMD for total hip and total spine regions for the 12-month time point were stable over the entire treatment period.

5.14 Effect on Growth

Orally inhaled corticosteroids may cause a reduction in growth velocity when administered to pediatric patients. Monitor the growth of pediatric patients receiving SYMBICORT routinely (e.g., via stadiometry). To minimize the systemic effects of orally inhaled corticosteroids, including SYMBICORT, titrate each patient's dose to the lowest dosage that effectively controls his/her symptoms [see Dosage and Administration (2.2) and Use in Specific Populations (8.4)].

5.15 Glaucoma and Cataracts

Glaucoma, increased intraocular pressure, and cataracts have been reported in patients with asthma and COPD following the long-term administration of inhaled corticosteroids, including budesonide, a component of SYMBICORT. Therefore, close monitoring is warranted in patients with a change in vision or with history of increased intraocular pressure, glaucoma, and/or cataracts.

Effects of treatment with SYMBICORT 160/4.5, SYMBICORT 80/4.5, formoterol 4.5 mcg, or placebo on development of cataracts or glaucoma were evaluated in a subset of 461 patients with COPD in the 12-month lung function study. Ophthalmic examinations were conducted at baseline, 24 weeks, and 52 weeks. There were 26 subjects (6%) with an increase in posterior subcapsular score from baseline to maximum value (>0.7) during the randomized treatment period. Changes in posterior subcapsular scores of >0.7 from baseline to treatment maximum occurred in 11 patients (9.0%) in the SYMBICORT 160/4.5 group, 4 patients (3.8%) in the SYMBICORT 80/4.5 group, 5 patients (4.2%) in the formoterol group, and 6 patients (5.2%) in the placebo group.

5.16 Eosinophilic Conditions and Churg-Strauss Syndrome

In rare cases, patients on inhaled corticosteroids may present with systemic eosinophilic conditions. Some of these patients have clinical features of vasculitis consistent with Churg-Strauss syndrome, a condition that is often treated with systemic corticosteroid therapy. These events usually, but not always, have been associated with the reduction and/or withdrawal of oral corticosteroid therapy following the introduction of inhaled corticosteroids. Physicians should be alert to eosinophilia, vasculitic rash, worsening pulmonary symptoms, cardiac complications, and/or neuropathy presenting in their patients. A causal relationship between budesonide and these underlying conditions has not been established.

5.17 Coexisting Conditions

SYMBICORT, like all medications containing sympathomimetic amines, should be used with caution in patients with convulsive disorders or thyrotoxicosis and in those who are unusually responsive to sympathomimetic amines. Doses of the related beta2-adrenoceptor agonist albuterol, when administered intravenously, have been reported to aggravate preexisting diabetes mellitus and ketoacidosis.

5.18 Hypokalemia and Hyperglycemia

Beta-adrenergic agonist medications may produce significant hypokalemia in some patients, possibly through intracellular shunting, which has the potential to produce adverse cardiovascular effects [see Clinical Pharmacology (12.2)]. The decrease in serum potassium is usually transient, not requiring supplementation. Clinically significant changes in blood glucose and/or serum potassium were seen infrequently during clinical studies with SYMBICORT at recommended doses.

6 ADVERSE REACTIONS

LABA use may result in the following:

- Serious asthma-related events – hospitalizations, intubations, death [see Warnings and Precautions (5.1)].
- Cardiovascular and central nervous system effects [see Warnings and Precautions (5.12)].

Systemic and inhaled corticosteroid use may result in the following:

- Candida albicans infection [see Warnings and Precautions (5.4)]
- Pneumonia or lower respiratory tract infections in patients with COPD [see Warnings and Precautions (5.5)]
- Immunosuppression [see Warnings and Precautions (5.6)]
- Hypercorticism and adrenal suppression [see Warnings and Precautions (5.8)]
- Growth effects in pediatric patients [see Warnings and Precautions (5.14)]
- Glaucoma and cataracts [see Warnings and Precautions (5.15)]

Because clinical trials are conducted under widely varying conditions, adverse reaction rates observed in the clinical trials of a drug cannot be directly compared to rates in the clinical trials of another drug and may not reflect the rates observed in practice.

6.1 Clinical Trials Experience in Asthma

Adult and Adolescent Patients 12 Years of Age and Older

The overall safety data in adults and adolescents are based upon 10 active- and placebo-controlled clinical trials in which 3393 patients ages 12 years and older (2052 females and 1341 males) with asthma of varying severity were treated with SYMBICORT 80/4.5 or 160/4.5 taken 2 inhalations once or twice daily for 12 to 52 weeks. In these trials, the patients on SYMBICORT had a mean age of 38 years and were predominantly Caucasian (82%).

The incidence of common adverse events in Table 2 below is based upon pooled data from three 12-week, double-blind, placebo-controlled clinical studies in which 401 adult and adolescent patients (148 males and 253 females) age 12 years and older were treated with 2 inhalations of SYMBICORT 80/4.5 or SYMBICORT 160/4.5 twice daily. The SYMBICORT group was composed of mostly Caucasian (84%) patients with a mean age of 38 years, and a mean percent predicted FEV1 at baseline of 76 and 68 for the 80/4.5 mcg and 160/4.5 mcg treatment groups, respectively. Control arms for comparison included 2 inhalations of budesonide HFA metered dose inhaler (MDI) 80 or 160 mcg, formoterol dry powder inhaler (DPI) 4.5 mcg, or placebo (MDI and DPI) twice daily. Table 2 includes all adverse events that occurred at an incidence of >3% in any one SYMBICORT group and more commonly than in the placebo group with twice-daily dosing. In considering these data, the increased average duration of patient exposure for SYMBICORT patients should be taken into account, as incidences are not adjusted for an imbalance of treatment duration.

Table 2 Adverse reactions occurring at an incidence of ≥ 3% and more commonly than placebo in the SYMBICORT groups: pooled data from three 12-week, double-blind, placebo-controlled clinical asthma trials in patients 12 years and older
Treatment [All treatments were administered as 2 inhalations twice daily.] | SYMBICORT |  | Budesonide |  | Formoterol | Placebo
Adverse Event | 80/4.5 N = 277 % | 160/4.5 N = 124 % | 80 mcg N = 121 % | 160 mcg N = 109 % | 4.5 mcg N = 237 % | N = 400 %
Nasopharyngitis | 10.5 | 9.7 | 14.0 | 11.0 | 10.1 | 9.0
Headache | 6.5 | 11.3 | 11.6 | 12.8 | 8.9 | 6.5
Upper respiratory tract infection | 7.6 | 10.5 | 8.3 | 9.2 | 7.6 | 7.8
Pharyngolaryngeal pain | 6.1 | 8.9 | 5.0 | 7.3 | 3.0 | 4.8
Sinusitis | 5.8 | 4.8 | 5.8 | 2.8 | 6.3 | 4.8
Influenza | 3.2 | 2.4 | 6.6 | 0.9 | 3.0 | 1.3
Back pain | 3.2 | 1.6 | 2.5 | 5.5 | 2.1 | 0.8
Nasal congestion | 2.5 | 3.2 | 2.5 | 3.7 | 1.3 | 1.0
Stomach discomfort | 1.1 | 6.5 | 2.5 | 4.6 | 1.3 | 1.8
Vomiting | 1.4 | 3.2 | 0.8 | 2.8 | 1.7 | 1.0
Oral Candidiasis | 1.4 | 3.2 | 0 | 0 | 0 | 0.8
Average Duration of Exposure (days) | 77.7 | 73.8 | 77.0 | 71.4 | 62.4 | 55.9

Long-term safety - asthma clinical trials in patients 12 years and older

Long-term safety studies in adolescent and adult patients 12 years of age and older, treated for up to 1 year at doses up to 1280/36 mcg/day (640/18 mcg twice daily), revealed neither clinically important changes in the incidence nor new types of adverse events emerging after longer periods of treatment. Similarly, no significant or unexpected patterns of abnormalities were observed for up to 1 year in safety measures including chemistry, hematology, ECG, Holter monitor, and HPA-axis assessments.

Pediatric Patients 6 to Less than 12 Years of Age

The safety data for pediatric patients aged 6 to less than 12 years is based on 1 trial of 12 weeks treatment duration. Patients (79 female and 105 male) receiving inhaled corticosteroid at trial entry were randomized to SYMBICORT 80/4.5 (n=92) or budesonide pMDI 80 mcg (n=92), 2 inhalations twice daily. The overall safety profile of these patients was similar to that observed in patients 12 years of age and older who received SYMBICORT 80/4.5 twice daily in studies of similar design. Common adverse reactions that occurred in patients treated with SYMBICORT 80/4.5 with a frequency of ≥3% and more frequently than patients treated only with budesonide pMDI 80 mcg included upper respiratory tract infection, pharyngitis, headache, and rhinitis.

6.2 Clinical Trials Experience in Chronic Obstructive Pulmonary Disease

The safety data described below reflect exposure to SYMBICORT 160/4.5 in 1783 patients. SYMBICORT 160/4.5 was studied in two placebo-controlled lung function studies (6 and 12 months in duration), and two active-controlled exacerbation studies (6 and 12 months in duration) in patients with COPD.

The incidence of common adverse events in Table 3 below is based upon pooled data from two double-blind, placebo-controlled lung function clinical studies (6 and 12 months in duration) in which 771 adult COPD patients (496 males and 275 females) 40 years of age and older were treated with SYMBICORT 160/4.5, two inhalations twice daily. Of these patients 651 were treated for 6 months and 366 were treated for 12 months. The SYMBICORT group was composed of mostly Caucasian (93%) patients with a mean age of 63 years, and a mean percent predicted FEV1 at baseline of 33%. Control arms for comparison included 2 inhalations of budesonide HFA (MDI) 160 mcg, formoterol (DPI) 4.5 mcg or placebo (MDI and DPI) twice daily. Table 3 includes all adverse events that occurred at an incidence of ≥3% in the SYMBICORT group and more commonly than in the placebo group. In considering these data, the increased average duration of patient exposure to SYMBICORT should be taken into account, as incidences are not adjusted for an imbalance of treatment duration.

Table 3 Adverse reactions occurring at an incidence of ≥ 3% and more commonly than placebo in the SYMBICORT group: pooled data from two double-blind, placebo-controlled clinical COPD trials
Treatment [All treatments were administered as 2 inhalations twice daily.] | SYMBICORT | Budesonide | Formoterol | Placebo
Adverse Event | 160/4.5; N = 771; % | 160 mcg; N = 275; % | 4.5 mcg; N = 779; % | N = 781; %
Nasopharyngitis | 7.3 | 3.3 | 5.8 | 4.9
Oral candidiasis | 6.0 | 4.4 | 1.2 | 1.8
Bronchitis | 5.4 | 4.7 | 4.5 | 3.5
Sinusitis | 3.5 | 1.5 | 3.1 | 1.8
Upper respiratory tract infection viral | 3.5 | 1.8 | 3.6 | 2.7
Average Duration of Exposure (days) | 255.2 | 157.1 | 240.3 | 223.7

Lung infections other than pneumonia (mostly bronchitis) occurred in a greater percentage of subjects treated with SYMBICORT 160/4.5 compared with placebo (7.9% vs. 5.1%, respectively). There were no clinically important or unexpected patterns of abnormalities observed for up to 1 year in chemistry, hematology, ECG, ECG (Holter) monitoring, HPA-axis, bone mineral density and ophthalmology assessments.

The safety findings from the two double-blind, active-controlled exacerbations studies (6 and 12 months in duration) in which 1012 adult COPD patients (616 males and 396 females) 40 years of age and older were treated with SYMBICORT 160/4.5, two inhalations twice daily were consistent with the lung function studies.

6.3 Postmarketing Experience

The following adverse reactions have been identified during post-approval use of SYMBICORT. Because these reactions are reported voluntarily from a population of uncertain size, it is not always possible to reliably estimate their frequency or establish a causal relationship to drug exposure. Some of these adverse reactions may also have been observed in clinical studies with SYMBICORT.

Cardiac disorders: angina pectoris, tachycardia, atrial and ventricular tachyarrhythmias, atrial fibrillation, extrasystoles, palpitations

Endocrine disorders: hypercorticism, growth velocity reduction in pediatric patients

Eye disorders: cataract, glaucoma, increased intraocular pressure

Gastrointestinal disorders: oropharyngeal candidiasis, nausea

Immune system disorders: immediate and delayed hypersensitivity reactions, such as anaphylactic reaction, angioedema, bronchospasm, urticaria, exanthema, dermatitis, pruritus

Metabolic and nutrition disorders: hyperglycemia, hypokalemia

Musculoskeletal, connective tissue, and bone disorders: muscle cramps

Nervous system disorders: tremor, dizziness

Psychiatric disorders: behavior disturbances, sleep disturbances, nervousness, agitation, depression, restlessness

Respiratory, thoracic, and mediastinal disorders: dysphonia, cough, throat irritation

Skin and subcutaneous tissue disorders: skin bruising

Vascular disorders: hypotension, hypertension

7 DRUG INTERACTIONS

In clinical studies, concurrent administration of SYMBICORT and other drugs, such as short-acting beta2-agonists, intranasal corticosteroids, and antihistamines/decongestants has not resulted in an increased frequency of adverse reactions. No formal drug interaction studies have been performed with SYMBICORT.

7.1 Inhibitors of Cytochrome P4503A4

The main route of metabolism of corticosteroids, including budesonide, a component of SYMBICORT, is via cytochrome P450 (CYP) isoenzyme 3A4 (CYP3A4). After oral administration of ketoconazole, a strong inhibitor of CYP3A4, the mean plasma concentration of orally administered budesonide increased. Concomitant administration of CYP3A4 may inhibit the metabolism of, and increase the systemic exposure to, budesonide. Caution should be exercised when considering the coadministration of SYMBICORT with long-term ketoconazole and other known strong CYP3A4 inhibitors (e.g., ritonavir, atazanavir, clarithromycin, indinavir, itraconazole, nefazodone, nelfinavir, saquinavir, telithromycin) [see Warnings and Precautions (5.9)].

7.2 Monoamine Oxidase Inhibitors and Tricyclic Antidepressants

SYMBICORT should be administered with caution to patients being treated with monoamine oxidase inhibitors or tricyclic antidepressants, or within 2 weeks of discontinuation of such agents, because the action of formoterol, a component of SYMBICORT, on the vascular system may be potentiated by these agents. In clinical trials with SYMBICORT, a limited number of COPD and asthma patients received tricyclic antidepressants, and, therefore, no clinically meaningful conclusions on adverse events can be made.

7.3 Beta-Adrenergic Receptor Blocking Agents

Beta-blockers (including eye drops) may not only block the pulmonary effect of beta-agonists, such as formoterol, a component of SYMBICORT, but may produce severe bronchospasm in patients with asthma. Therefore, patients with asthma should not normally be treated with beta-blockers. However, under certain circumstances, there may be no acceptable alternatives to the use of beta-adrenergic blocking agents in patients with asthma. In this setting, cardioselective beta-blockers could be considered, although they should be administered with caution.

7.4 Diuretics

The ECG changes and/or hypokalemia that may result from the administration of non-potassium-sparing diuretics (such as loop or thiazide diuretics) can be acutely worsened by beta-agonists, especially when the recommended dose of the beta-agonist is exceeded. Although the clinical significance of these effects is not known, caution is advised in the coadministration of SYMBICORT with non-potassium-sparing diuretics.

8 USE IN SPECIFIC POPULATIONS

8.1 Pregnancy

Risk Summary

There are no adequate and well-controlled studies of SYMBICORT or one of its individual components, formoterol fumarate, in pregnant women; however studies are available for the other component budesonide. In animal reproduction studies, SYMBICORT, administered by the inhalation route, was teratogenic, embryocidal, and reduced fetal weights in rats at less than the maximum recommended human daily inhalation dose (MRHDID) on a mcg/m^2 basis. Budesonide alone, administered by the subcutaneous route, was teratogenic, embryocidal, and reduced fetal weights in rats and rabbits at less than the MRHDID, but these effects were not seen in rats that received inhaled doses up to 4 times the MRHDID. Studies of pregnant women have not shown that inhaled budesonide alone increases the risk of abnormalities when administered during pregnancy. Experience with oral corticosteroids suggests that rodents are more prone to teratogenic effects from corticosteroid exposure than humans. Formoterol fumarate alone, administered by the oral route, was teratogenic in rats and rabbits at 1600 and 65,000 times the MRHDID, respectively. Formoterol fumarate was also embryocidal, increased pup loss at birth and during lactation, and decreased pup weight in rats at 110 times the MRHDID. These adverse effects generally occurred at large multiples of the MRHDID when formoterol fumarate was administered by the oral route to achieve high systemic exposures. No teratogenic, embryocidal, or developmental effects were seen in rats that received inhalation doses up to 375 times the MRHDID.

The estimated background risk of major birth defects and miscarriage of the indicated populations is unknown. In the U.S. general population, the estimated background risk of major birth defects and miscarriage in clinically recognized pregnancies is 2% to 4% and 15% to 20%, respectively.

Clinical Considerations

Disease-Associated Maternal and/or Embryo/Fetal risk

In women with poorly or moderately controlled asthma, there is an increased risk of several perinatal adverse outcomes such as preeclampsia in the mother and prematurity, low birth weight, and small for gestational age in the neonate. Pregnant women with asthma should be closely monitored and medication adjusted as necessary to maintain optimal asthma control.

Labor or Delivery

There are no well-controlled human studies that have investigated the effects of SYMBICORT during labor and delivery. Because of the potential for beta-agonist interference with uterine contractility, use of SYMBICORT during labor should be restricted to those patients in whom the benefits clearly outweigh the risk.

Data

Human Data

Studies of pregnant women have not shown that inhaled budesonide increases the risk of abnormalities when administered during pregnancy. The results from a large population-based prospective cohort epidemiological study reviewing data from three Swedish registries covering approximately 99% of the pregnancies from 1995-1997 (i.e., Swedish Medical Birth Registry; Registry of Congenital Malformations; Child Cardiology Registry) indicate no increased risk for congenital malformations from the use of inhaled budesonide during early pregnancy. Congenital malformations were studied in 2014 infants born to mothers reporting the use of inhaled budesonide for asthma in early pregnancy (usually 10-12 weeks after the last menstrual period), the period when most major organ malformations occur. The rate of recorded congenital malformations was similar compared to the general population rate (3.8% vs. 3.5%, respectively). In addition, after exposure to inhaled budesonide, the number of infants born with orofacial clefts was similar to the expected number in the normal population (4 children vs. 3.3, respectively).

These same data were utilized in a second study bringing the total to 2534 infants whose mothers were exposed to inhaled budesonide. In this study, the rate of congenital malformations among infants whose mothers were exposed to inhaled budesonide during early pregnancy was not different from the rate for all newborn babies during the same period (3.6%).

Animal Data

SYMBICORT

In an embryo-fetal development study in pregnant rats dosed during the period of organogenesis from gestation days 6-16, SYMBICORT produced umbilical hernia in fetuses at doses less than the MRHDID (on a mcg/m^2 basis at maternal inhaled doses of 12/0.66 mcg/kg/day and above). Fetal weights were reduced at approximately 5 and 3 times the MRHDID, respectively (on an AUC basis at a maternal inhaled dose of 80/4.4 mcg/kg (budesonide/formoterol)). No teratogenic or embryocidal effects were detected at doses less than the MRHDID (on a mcg/m^2 basis at a maternal inhaled dose of 2.5/0.14 mcg/kg/day).

Budesonide

In a fertility and reproduction study, male rats were subcutaneously dosed for 9 weeks and females for 2 weeks prior to pairing and throughout the mating period. Females were dosed up until weaning of their offspring. Budesonide caused a decrease in prenatal viability and viability in the pups at birth and during lactation, along with a decrease in maternal body-weight gain, at doses less than the MRHDID (on a mcg/m^2 basis at maternal subcutaneous doses of 20 mcg/kg/day and above). No such effects were noted at a dose less than the MRHDID (on a mcg/m^2 basis at a maternal subcutaneous dose of 5 mcg/kg/day).

In an embryo-fetal development study in pregnant rabbits dosed during the period of organogenesis from gestation days 6-18, budesonide produced fetal loss, decreased fetal weight, and skeletal abnormalities at doses less than the MRHDID (on a mcg/m^2 basis at a maternal subcutaneous dose of 25 mcg/kg/day). In an embryo-fetal development study in pregnant rats dosed during the period of organogenesis from gestation days 6-15, budesonide produced similar adverse fetal effects at doses approximately 8 times the MRHDID (on a mcg/m^2 basis at a maternal subcutaneous dose of 500 mcg/kg/day). In another embryo-fetal development study in pregnant rats, no teratogenic or embryocidal effects were seen at doses up to 4 times the MRHDID (on a mcg/m^2 basis at maternal inhalation doses up to 250 mcg/kg/day).

In a peri-and post-natal development study, rats dosed from gestation day 15 to postpartum day 21, budesonide had no effects on delivery, but did have an effect on growth and development of offspring. Offspring survival was reduced and surviving offspring had decreased mean body weights at birth and during lactation at doses less than the MRHDID and higher (on a mcg/m^2 basis at maternal subcutaneous doses of 20 mcg/kg/day and higher). These findings occurred in the presence of maternal toxicity.

Formoterol

In a fertility and reproduction study, male rats were orally dosed for 9 weeks and females for 2 weeks prior to pairing and throughout the mating period. Females were either dosed up to gestation day 19 or up until weaning of their offspring. Males were dosed up to 25 weeks. Umbilical hernia was observed in rat fetuses at oral doses 1600 times and greater than the MRHDID (on a mcg/m^2 basis at maternal oral doses of 3000 mcg/kg/day and higher). Brachygnathia was observed in rat fetuses at a dose 8000 times the MRHDID (on a mcg/m^2 basis at a maternal oral dose of 15,000 mcg/kg/day). Pregnancy was prolonged at a dose 8000 times the MRHDID (on a mcg/m^2 basis at a maternal oral dose of 15,000 mcg/kg/day). Fetal and pup deaths occurred at doses approximately 1600 times the MRHDID and higher (on a mcg/m^2 basis at oral doses of 3000 mcg/kg/day and higher) during gestation.

In an embryo-fetal development study in pregnant rats dosed during the period of organogenesis from gestation days 6-15, no teratogenic, embryocidal or developmental effects were seen at doses up to 375 times the MRHDID (on a mcg/m^2 basis with maternal inhalation doses up to 690 mcg/kg/day).

In an embryo-fetal development study in pregnant rabbits dosed during the period of organogenesis from gestation days 6-18, subcapsular cysts on the liver were observed in the fetuses at a dose 65,000 times the MRHDID (on a mcg/m^2 basis with a maternal oral dose of 60,000 mcg/kg/day). No teratogenic effects were observed at doses up to 3800 times the MRHDID (on a mcg/m^2 basis at maternal oral doses up to 3500 mcg/kg/day).

In a pre- and post-natal development study, pregnant female rats received formoterol at oral doses of 0, 210, 840, and 3400 mcg/kg/day from gestation day 6 through the lactation period. Pup survival was decreased from birth to postpartum day 26 at doses 110 times the MRHDID and higher (on a mcg/m^2 basis at maternal oral doses of 210 mcg/kg/day and higher), although there was no evidence of a dose- response relationship. There were no treatment-related effects on the physical, functional, and behavioral development of rat pups.

8.2 Lactation

Risk Summary

There are no available data on the effects of SYMBICORT, budesonide or formoterol fumarate on the breastfed child or on milk production. Budesonide, like other inhaled corticosteroids, is present in human milk [see Data]. There are no available data on the presence of formoterol fumarate in human milk. Formoterol fumarate is present in rat milk [see Data]. The developmental and health benefits of breastfeeding should be considered along with the mother’s clinical need for SYMBICORT and any potential adverse effects on the breastfed infant from SYMBICORT or from the underlying maternal condition.

Data

Human data with budesonide delivered via dry powder inhaler indicates that the total daily oral dose of budesonide available in breast milk to the infant is approximately 0.3% to 1% of the dose inhaled by the mother [see Clinical Pharmacology (12.3)]. For SYMBICORT, the dose of budesonide available to the infant in breast milk, as a percentage of the maternal dose, would be expected to be similar.

In the fertility and reproduction study in rats, plasma levels of formoterol were measured in pups on post-natal day 15 [see Use in Specific Populations (8.1)]. It was estimated that the maximum plasma concentration that the pups received from the maternal animal, at the highest dose of 15 mg/kg, after nursing was 4.4% (0.24 nmol/L for a litter vs. 5.5 nmol/L for the mother).

8.4 Pediatric Use

Safety and effectiveness of SYMBICORT in asthma patients 12 years of age and older have been established in studies up to 12 months. In the two 12-week, double-blind, placebo-controlled US pivotal studies 25 patients 12 to 17 years of age were treated with SYMBICORT twice daily [see Clinical Studies (14.1)]. Efficacy results in this age group were similar to those observed in patients 18 years and older. There were no obvious differences in the type or frequency of adverse events reported in this age group compared with patients 18 years of age and older.

The safety and effectiveness of SYMBICORT 80/4.5 in asthma patients 6 to less than 12 years of age have been established in studies of up to 12-week duration [see Clinical Studies (14.1)]. The safety profile in these patients was consistent to that observed in patients 12 years of age and older who also received SYMBICORT [see Adverse Reactions (6.1)].

The safety and effectiveness of SYMBICORT in asthma patients less than 6 years of age have not been established.

Controlled clinical studies have shown that orally inhaled corticosteroids including budesonide, a component of SYMBICORT, may cause a reduction in growth velocity in pediatric patients. This effect has been observed in the absence of laboratory evidence of HPA-axis suppression, suggesting that growth velocity is a more sensitive indicator of systemic corticosteroid exposure in pediatric patients than some commonly used tests of HPA-axis function. The long-term effect of this reduction in growth velocity associated with orally inhaled corticosteroids, including the impact on final height are unknown. The potential for “catch-up” growth following discontinuation of treatment with orally inhaled corticosteroids has not been adequately studied.

In a study of asthmatic children 5 to 12 years of age, those treated with budesonide DPI 200 mcg twice daily (n=311) had a 1.1 centimeter reduction in growth compared with those receiving placebo (n=418) at the end of one year; the difference between these two treatment groups did not increase further over three years of additional treatment. By the end of 4 years, children treated with budesonide DPI and children treated with placebo had similar growth velocities. Conclusions drawn from this study may be confounded by the unequal use of corticosteroids in the treatment groups and inclusion of data from patients attaining puberty during the course of the study.

The growth of pediatric patients receiving orally inhaled corticosteroids, including SYMBICORT, should be monitored. If a child or adolescent on any corticosteroid appears to have growth suppression, the possibility that he/she is particularly sensitive to this effect should be considered. The potential growth effects of prolonged treatment should be weighed against the clinical benefits obtained. To minimize the systemic effects of orally inhaled corticosteroids, including SYMBICORT, each patient should be titrated to the lowest strength that effectively controls his/her asthma [see Dosage and Administration (2)].

8.5 Geriatric Use

Of the total number of asthma patients treated with SYMBICORT twice daily in two 12-week studies and a 26-week postmarketing study, 791 were 65 years of age or older, of whom 141 were 75 years of age or older.

In the COPD studies of 6 to 12 months duration, 810 patients treated with SYMBICORT 160/4.5, two inhalations twice daily were 65 years old and above and of those, 177 patients were 75 years of age and older. No overall differences in safety or effectiveness were observed between these patients and younger patients, and other reported clinical experience has not identified differences in responses between the elderly and younger patients.

As with other products containing beta2-agonists, special caution should be observed when using SYMBICORT in geriatric patients who have concomitant cardiovascular disease that could be adversely affected by beta2-agonists.

Based on available data for SYMBICORT or its active components, no adjustment of dosage of SYMBICORT in geriatric patients is warranted.

8.6 Hepatic Impairment

Formal pharmacokinetic studies using SYMBICORT have not been conducted in patients with hepatic impairment. However, since both budesonide and formoterol fumarate are predominantly cleared by hepatic metabolism, impairment of liver function may lead to accumulation of budesonide and formoterol fumarate in plasma. Therefore, patients with hepatic disease should be closely monitored.

8.7 Renal Impairment

Formal pharmacokinetic studies using SYMBICORT have not been conducted in patients with renal impairment.

10 OVERDOSAGE

SYMBICORT

SYMBICORT contains both budesonide and formoterol; therefore, the risks associated with overdosage for the individual components described below apply to SYMBICORT. In pharmacokinetic studies, single doses of 960/54 mcg (12 actuations of SYMBICORT 80/4.5) and 1280/36 mcg (8 actuations of 160/4.5), were administered to patients with COPD. A total of 1920/54 mcg (12 actuations of SYMBICORT 160/4.5) was administered as a single dose to both healthy subjects and patients with asthma. In a long-term active-controlled safety study in adolescent and adult asthma patients 12 years of age and older, SYMBICORT 160/4.5 was administered for up to 12 months at doses up to twice the highest recommended daily dose. There were no clinically significant adverse reactions observed in any of these studies.

Budesonide

The potential for acute toxic effects following overdose of budesonide is low. If used at excessive doses for prolonged periods, systemic corticosteroid effects such as hypercorticism may occur [see Warnings and Precautions (5)]. Budesonide at five times the highest recommended dose (3200 mcg daily) administered to humans for 6 weeks caused a significant reduction (27%) in the plasma cortisol response to a 6-hour infusion of ACTH compared with placebo (+1%). The corresponding effect of 10 mg prednisone daily was a 35% reduction in the plasma cortisol response to ACTH.

Formoterol

An overdose of formoterol would likely lead to an exaggeration of effects that are typical for beta2-agonists: seizures, angina, hypertension, hypotension, tachycardia, atrial and ventricular tachyarrhythmias, nervousness, headache, tremor, palpitations, muscle cramps, nausea, dizziness, sleep disturbances, metabolic acidosis, hyperglycemia, hypokalemia. As with all sympathomimetic medications, cardiac arrest and even death may be associated with abuse of formoterol. No clinically significant adverse reactions were seen when formoterol was delivered to adult patients with acute bronchoconstriction at a dose of 90 mcg/day over 3 hours or to stable asthmatics 3 times a day at a total dose of 54 mcg/day for 3 days.

Treatment of formoterol overdosage consists of discontinuation of the medication together with institution of appropriate symptomatic and/or supportive therapy. The judicious use of a cardioselective beta-receptor blocker may be considered, bearing in mind that such medication can produce bronchospasm. There is insufficient evidence to determine if dialysis is beneficial for overdosage of formoterol. Cardiac monitoring is recommended in cases of overdosage.

11 DESCRIPTION

SYMBICORT 80/4.5 and SYMBICORT 160/4.5 each contain micronized budesonide and micronized formoterol fumarate dihydrate for oral inhalation only.

Each SYMBICORT 80/4.5 and SYMBICORT 160/4.5 canister is formulated as a hydrofluoroalkane (HFA 227; 1,1,1,2,3,3,3-heptafluoropropane)-propelled pressurized metered dose inhaler containing either 60 or 120 actuations [see Dosage Forms and Strengths (3) and How Supplied/Storage and Handling (16)]. After priming, each actuation meters either 91/5.1 mcg or 181/5.1 mcg from the valve and delivers either 80/4.5 mcg, or 160/4.5 mcg (budesonide micronized/formoterol fumarate dihydrate micronized) from the actuator. The actual amount of drug delivered to the lung may depend on patient factors, such as the coordination between actuation of the device and inspiration through the delivery system. SYMBICORT also contains povidone K25 USP as a suspending agent and polyethylene glycol 1000 NF as a lubricant.

SYMBICORT should be primed before using for the first time by releasing two test sprays into the air away from the face, shaking well for 5 seconds before each spray. In cases where the inhaler has not been used for more than 7 days or when it has been dropped, prime the inhaler again by shaking well for 5 seconds before each spray and releasing two test sprays into the air away from the face.

One active component of SYMBICORT is budesonide, a corticosteroid designated chemically as (RS)-11β, 16α, 17,21-Tetrahydroxypregna-1,4-diene-3,20-dione cyclic 16,17-acetal with butyraldehyde. Budesonide is provided as a mixture of two epimers (22R and 22S). The empirical formula of budesonide is C25H34O6 and its molecular weight is 430.5. Its structural formula is:

Budesonide is a white to off-white, tasteless, odorless powder which is practically insoluble in water and in heptane, sparingly soluble in ethanol, and freely soluble in chloroform. Its partition coefficient between octanol and water at pH 7.4 is 1.6 x 10^3.

The other active component of SYMBICORT is formoterol fumarate dihydrate, a selective beta2-agonist designated chemically as (R*,R*)-(±)-N-[2-hydroxy-5-[1-hydroxy-2-[[2-(4-methoxyphenyl)-1-methylethyl]amino]ethyl]phenyl]formamide, (E)-2-butendioate(2:1), dihydrate. The empirical formula of formoterol is C42H56N4O14 and its molecular weight is 840.9. Its structural formula is:

Formoterol fumarate dihydrate is a powder which is slightly soluble in water. Its octanol-water partition coefficient at pH 7.4 is 2.6. The pKa of formoterol fumarate dihydrate at 25°C is 7.9 for the phenolic group and 9.2 for the amino group.

12 CLINICAL PHARMACOLOGY

12.1 Mechanism of Action

SYMBICORT

SYMBICORT contains both budesonide and formoterol; therefore, the mechanisms of action described below for the individual components apply to SYMBICORT. These drugs represent two classes of medications (a synthetic corticosteroid and a long-acting selective beta2-adrenoceptor agonist) that have different effects on clinical, physiological, and inflammatory indices of COPD and asthma.

Budesonide

Budesonide is an anti-inflammatory corticosteroid that exhibits potent glucocorticoid activity and weak mineralocorticoid activity. In standard in vitro and animal models, budesonide has approximately a 200-fold higher affinity for the glucocorticoid receptor and a 1000-fold higher topical anti-inflammatory potency than cortisol (rat croton oil ear edema assay). As a measure of systemic activity, budesonide is 40 times more potent than cortisol when administered subcutaneously and 25 times more potent when administered orally in the rat thymus involution assay.

In glucocorticoid receptor affinity studies, the 22R form of budesonide was two times as active as the 22S epimer. In vitro studies indicated that the two forms of budesonide do not interconvert.

Inflammation is an important component in the pathogenesis of COPD and asthma. Corticosteroids have a wide range of inhibitory activities against multiple cell types (e.g., mast cells, eosinophils, neutrophils, macrophages, and lymphocytes) and mediators (e.g., histamine, eicosanoids, leukotrienes, and cytokines) involved in allergic and non–allergic-mediated inflammation. These anti-inflammatory actions of corticosteroids may contribute to their efficacy in COPD and asthma.

Studies in asthmatic patients have shown a favorable ratio between topical anti-inflammatory activity and systemic corticosteroid effects over a wide range of doses of budesonide. This is explained by a combination of a relatively high local anti-inflammatory effect, extensive first pass hepatic degradation of orally absorbed drug (85%-95%), and the low potency of formed metabolites.

Formoterol

Formoterol fumarate is a long-acting selective beta2-adrenergic agonist (beta2-agonist) with a rapid onset of action. Inhaled formoterol fumarate acts locally in the lung as a bronchodilator. In vitro studies have shown that formoterol has more than 200-fold greater agonist activity at beta2-receptors than at beta1-receptors. The in vitro binding selectivity to beta2- over beta1-adrenoceptors is higher for formoterol than for albuterol (5 times), whereas salmeterol has a higher (3 times) beta2-selectivity ratio than formoterol.

Although beta2-receptors are the predominant adrenergic receptors in bronchial smooth muscle and beta1-receptors are the predominant receptors in the heart, there are also beta2-receptors in the human heart comprising 10% to 50% of the total beta-adrenergic receptors. The precise function of these receptors has not been established, but they raise the possibility that even highly selective beta2-agonists may have cardiac effects.

The pharmacologic effects of beta2-adrenoceptor agonist drugs, including formoterol, are at least in part attributable to stimulation of intracellular adenyl cyclase, the enzyme that catalyzes the conversion of adenosine triphosphate (ATP) to cyclic-3', 5'-adenosine monophosphate (cyclic AMP). Increased cyclic AMP levels cause relaxation of bronchial smooth muscle and inhibition of release of mediators of immediate hypersensitivity from cells, especially from mast cells.

In vitro tests show that formoterol is an inhibitor of the release of mast cell mediators, such as histamine and leukotrienes, from the human lung. Formoterol also inhibits histamine-induced plasma albumin extravasation in anesthetized guinea pigs and inhibits allergen-induced eosinophil influx in dogs with airway hyper-responsiveness. The relevance of these in vitro and animal findings to humans is unknown.

12.2 Pharmacodynamics

Asthma

Cardiovascular effects: In a single-dose cross-over study involving 201 patients with persistent asthma, single-dose treatments of 4.5, 9, and 18 mcg of formoterol in combination with 320 mcg of budesonide delivered via SYMBICORT were compared to budesonide 320 mcg alone. Dose-ordered improvements in FEV1 were demonstrated when compared with budesonide. ECGs and blood samples for glucose and potassium were obtained post-dose. For SYMBICORT, small mean increases in serum glucose and decreases in serum potassium (+0.44 mmol/L and -0.18 mmol/L at the highest dose, respectively) were observed with increasing doses of formoterol, compared to budesonide. In ECGs, SYMBICORT produced small dose-related mean increases in heart rate (approximately 3 bpm at the highest dose), and QTc intervals (3-6 msec) compared to budesonide alone. No subject had a QT or QTc value ≥500 msec.

In the United States, five 12-week, active- and placebo-controlled studies and one 6-month active-controlled study evaluated 2976 patients aged 6 years and older with asthma. Systemic pharmacodynamic effects of formoterol (heart/pulse rate, blood pressure, QTc interval, potassium, and glucose) were similar in patients treated with SYMBICORT, compared with patients treated with formoterol dry inhalation powder 4.5 mcg, 2 inhalations twice daily. No patient had a QT or QTc value ≥500 msec during treatment.

In three placebo-controlled studies in adolescents and adults with asthma, aged 12 years and older, a total of 1232 patients (553 patients in the SYMBICORT group) had evaluable continuous 24-hour electrocardiographic monitoring. Overall, there were no important differences in the occurrence of ventricular or supraventricular ectopy and no evidence of increased risk for clinically significant dysrhythmia in the SYMBICORT group compared to placebo.

HPA-axis effects: Overall, no clinically important effects on HPA-axis, as measured by 24-hour urinary cortisol, were observed for SYMBICORT treated adult or adolescent patients at doses up to 640/18 mcg/day compared to budesonide.

Chronic Obstructive Pulmonary Disease

Cardiovascular effects: In two COPD lung function studies, 6 months and 12 months in duration including 3668 COPD patients, no clinically important differences were seen in pulse rate, blood pressure, potassium, and glucose between SYMBICORT, the individual components of SYMBICORT, and placebo [see Clinical Studies (14.2)].

ECGs recorded at multiple clinic visits on treatment in both studies showed no clinically important differences for heart rate, PR interval, QRS duration, heart rate, signs of cardiac ischemia or arrhythmias between SYMBICORT 160/4.5 the monoproducts and placebo, all administered as 2 inhalations twice daily. Based on ECGs, 6 patients treated with SYMBICORT 160/4.5, 6 patients treated with formoterol 4.5 mcg, and 6 patients in the placebo group experienced atrial fibrillation or flutter that was not present at baseline. There were no cases of nonsustained ventricular tachycardia in the SYMBICORT 160/4.5, formoterol 4.5 mcg, or placebo groups.

In the 12-month study, 520 patients had evaluable continuous 24-hour ECG (Holter) monitoring prior to the first dose and after approximately 1 and 4 months on treatment. No clinically important differences in ventricular or supraventricular arrhythmias, ventricular or supraventricular ectopic beats, or heart rate were observed among the groups treated with SYMBICORT 160/4.5, formoterol or placebo taken as 2 inhalations twice daily. Based on ECG (Holter) monitoring, one patient on SYMBICORT 160/4.5, no patients on formoterol 4.5 mcg, and three patients in the placebo group experienced atrial fibrillation or flutter that was not present at baseline.

HPA-axis effects: Twenty-four hour urinary cortisol measurements were collected in a pooled subset (n=616) of patients from two COPD lung function studies. The data indicated approximately 30% lower mean 24-hour urinary free cortisol values following chronic administration (> 6 months) of SYMBICORT relative to placebo. SYMBICORT appeared to exhibit comparable cortisol suppression to budesonide 160 mcg alone or coadministration of budesonide 160 mcg and formoterol 4.5 mcg. For patients treated with SYMBICORT or placebo for up to 12 months, the percentage of patients who shifted from normal to low for this measure were generally comparable.

Other Budesonide Products

To confirm that systemic absorption is not a significant factor in the clinical efficacy of inhaled budesonide, a clinical study in patients with asthma was performed comparing 400 mcg budesonide administered via a pressurized metered dose inhaler with a tube spacer to 1400 mcg of oral budesonide and placebo. The study demonstrated the efficacy of inhaled budesonide but not orally ingested budesonide, despite comparable systemic levels. Thus, the therapeutic effect of conventional doses of orally inhaled budesonide are largely explained by its direct action on the respiratory tract.

Inhaled budesonide has been shown to decrease airway reactivity to various challenge models, including histamine, methacholine, sodium metabisulfite, and adenosine monophosphate in patients with hyperreactive airways. The clinical relevance of these models is not certain.

Pretreatment with inhaled budesonide, 1600 mcg daily (800 mcg twice daily) for 2 weeks reduced the acute (early-phase reaction) and delayed (late-phase reaction) decrease in FEV1 following inhaled allergen challenge.

The systemic effects of inhaled corticosteroids are related to the systemic exposure to such drugs. Pharmacokinetic studies have demonstrated that in both adults and children with asthma the systemic exposure to budesonide is lower with SYMBICORT compared with inhaled budesonide administered at the same delivered dose via a dry powder inhaler [see Clinical Pharmacology (12.3)]. Therefore, the systemic effects (HPA-axis and growth) of budesonide delivered from SYMBICORT would be expected to be no greater than what is reported for inhaled budesonide when administered at comparable doses via the dry powder inhaler [see Use in Specific Populations (8.4)].

HPA-axis effects: The effects of inhaled budesonide administered via a dry powder inhaler on the HPA-axis were studied in 905 adults and 404 pediatric patients with asthma. For most patients, the ability to increase cortisol production in response to stress, as assessed by cosyntropin (ACTH) stimulation test, remained intact with budesonide treatment at recommended doses. For adult patients treated with 100, 200, 400, or 800 mcg twice daily for 12 weeks, 4%, 2%, 6%, and 13%, respectively, had an abnormal stimulated cortisol response (peak cortisol <14.5 mcg/dL assessed by liquid chromatography following short-cosyntropin test) as compared to 8% of patients treated with placebo. Similar results were obtained in pediatric patients. In another study in adults, doses of 400, 800, and 1600 mcg of inhaled budesonide twice daily for 6 weeks were examined; 1600 mcg twice daily (twice the maximum recommended dose) resulted in a 27% reduction in stimulated cortisol (6-hour ACTH infusion) while 10-mg prednisone resulted in a 35% reduction. In this study, no patient on budesonide at doses of 400 and 800 mcg twice daily met the criterion for an abnormal stimulated-cortisol response (peak cortisol <14.5 mcg/dL assessed by liquid chromatography) following ACTH infusion. An open-label, long-term follow-up of 1133 patients for up to 52 weeks confirmed the minimal effect on the HPA-axis (both basal- and stimulated-plasma cortisol) of budesonide when administered at recommended doses. In patients who had previously been oral-steroid-dependent, use of budesonide in recommended doses was associated with higher stimulated-cortisol response compared to baseline following 1 year of therapy.

Other Formoterol Products

While the pharmacodynamic effect is via stimulation of beta-adrenergic receptors, excessive activation of these receptors commonly leads to skeletal muscle tremor and cramps, insomnia, tachycardia, decreases in plasma potassium, and increases in plasma glucose. Inhaled formoterol, like other beta2-adrenergic agonist drugs, can produce dose-related cardiovascular effects and effects on blood glucose and/or serum potassium [see Warnings and Precautions (5)]. For SYMBICORT, these effects are detailed in the Clinical Pharmacology, Pharmacodynamics, SYMBICORT (12.2) section.

Use of LABA drugs can result in tolerance to bronchoprotective and bronchodilatory effects.

Rebound bronchial hyperresponsiveness after cessation of chronic long-acting beta-agonist therapy has not been observed.

12.3 Pharmacokinetics

SYMBICORT

Absorption

Budesonide
Healthy Subjects: Orally inhaled budesonide is rapidly absorbed in the lungs and peak concentration is typically reached within 20 minutes. After oral administration of budesonide peak plasma concentration was achieved in about 1 to 2 hours and the absolute systemic availability was 6%-13% due to extensive first pass metabolism. In contrast, most of the budesonide delivered to the lungs was systemically absorbed. In healthy subjects, 34% of the metered dose was deposited in the lung (as assessed by plasma concentration method and using a budesonide-containing dry powder inhaler) with an absolute systemic availability of 39% of the metered dose.

Following administration of SYMBICORT 160/4.5, two or four inhalations twice daily for 5 days in healthy subjects, plasma concentration of budesonide generally increased in proportion to dose. The accumulation index for the group that received 2 inhalations twice daily was 1.32 for budesonide.

Asthma Patients: In a single-dose study, higher than recommended doses of SYMBICORT (12 inhalations of SYMBICORT 160/4.5) were administered to patients with moderate asthma. Peak budesonide plasma concentration of 4.5 nmol/L occurred at 20 minutes following dosing. This study demonstrated that the total systemic exposure to budesonide from SYMBICORT was approximately 30% lower than from inhaled budesonide via a dry powder inhaler (DPI) at the same delivered dose. Following administration of SYMBICORT, the half-life of the budesonide component was 4.7 hours.

In a repeat dose study, the highest recommended dose of SYMBICORT (160/4.5, two inhalations twice daily) was administered to patients with moderate asthma and healthy subjects for 1 week. Peak budesonide plasma concentration of 1.2 nmol/L occurred at 21 minutes in asthma patients. Peak budesonide plasma concentration was 27% lower in asthma patients compared to that in healthy subjects. However, the total systemic exposure of budesonide was comparable to that in asthma patients.

Peak steady-state plasma concentrations of budesonide administered by DPI in adults with asthma averaged 0.6 and 1.6 nmol/L at doses of 180 mcg and 360 mcg twice daily, respectively. In asthmatic patients, budesonide showed a linear increase in AUC and Cmax with increasing dose after both single and repeated dosing of inhaled budesonide.

COPD Patients: In a single-dose study, 12 inhalations of SYMBICORT 80/4.5 (total dose 960/54 mcg) were administered to patients with COPD. Mean budesonide peak plasma concentration of 3.3 nmol/L occurred at 30 minutes following dosing. Budesonide systemic exposure was comparable between SYMBICORT pMDI and coadministration of budesonide via a metered-dose inhaler and formoterol via a dry powder inhaler (budesonide 960 mcg and formoterol 54 mcg). In the same study, an open-label group of moderate asthma patients also received the same higher dose of SYMBICORT. For budesonide, COPD patients exhibited 12% greater AUC and 10% lower Cmax compared to asthma patients.

In the 6-month pivotal lung function clinical study, steady-state pharmacokinetic data of budesonide was obtained in a subset of COPD patients with treatment arms of SYMBICORT pMDI 160/4.5, SYMBICORT pMDI 80/4.5, budesonide 160 mcg, budesonide 160 mcg and formoterol 4.5 mcg given together, all administered as 2 inhalations twice daily. Budesonide systemic exposure (AUC and Cmax) increased proportionally with doses from 80 mcg to 160 mcg and was generally similar between the 3 treatment groups receiving the same dose of budesonide (SYMBICORT pMDI 160/4.5, budesonide 160 mcg, budesonide 160 mcg and formoterol 4.5 mcg administered together).

Formoterol

Inhaled formoterol is rapidly absorbed; peak plasma concentrations are typically reached at the first plasma sampling time, within 5-10 minutes after dosing. As with many drug products for oral inhalation, it is likely that the majority of the inhaled formoterol delivered is swallowed and then absorbed from the gastrointestinal tract.

Healthy Subjects: Following administration of SYMBICORT (160/4.5, two or four inhalations twice daily) for 5 days in healthy subjects, plasma concentration of formoterol generally increased in proportion to dose. The accumulation index for the group that received 2 inhalations twice daily was 1.77 for formoterol.

Asthma patients: In a single-dose study, higher than recommended doses of SYMBICORT (12 inhalations of SYMBICORT 160/4.5) were administered to patients with moderate asthma. Peak plasma concentration for formoterol of 136 pmol occurred at 10 minutes following dosing. Approximately 8% of the delivered dose of formoterol was recovered in the urine as unchanged drug.

In a repeat dose study, the highest recommended dose of SYMBICORT (160/4.5, two inhalations twice daily) was administered to patients with moderate asthma and healthy subjects for 1 week. Peak formoterol plasma concentration of 28 pmol/L occurred at 10 minutes in asthma patients. Peak formoterol plasma concentration was about 42% lower in asthma patients compared to that in healthy subjects. However, the total systemic exposure of formoterol was comparable to that in asthma patients.

COPD patients: Following single-dose administration of 12 inhalations of SYMBICORT 80/4.5, mean peak formoterol plasma concentration of 167 pmol/L was rapidly achieved at 15 minutes after dosing. Formoterol exposure was slightly greater (~16-18%) from SYMBICORT pMDI compared to coadministration of budesonide via a metered-dose inhaler and formoterol via a dry powder inhaler (total dose of budesonide 960 mcg and formoterol 54 mcg). In the same study, an open label group of moderate asthma patients received the same dose of SYMBICORT. COPD patients exhibited 12-15% greater AUC and Cmax for formoterol compared to asthma patients.

In the 6-month pivotal lung function clinical study, steady-state pharmacokinetic data of formoterol was obtained in a subset of COPD patients with treatment arms of SYMBICORT pMDI 160/4.5, SYMBICORT pMDI 80/4.5, formoterol 4.5 mcg, budesonide 160 mcg and formoterol 4.5 mcg given together, all administered as 2 inhalations twice daily. The systemic exposure of formoterol as evidenced by AUC, was about 30% and 16% higher from SYMBICORT pMDI compared to formoterol alone treatment arm and coadministration of individual components of budesonide and formoterol treatment arm, respectively.

Distribution
Budesonide: The volume of distribution of budesonide was approximately 3 L/kg. It was 85%-90% bound to plasma proteins. Protein binding was constant over the concentration range (1-100 nmol/L) achieved with, and exceeding, recommended inhaled doses. Budesonide showed little or no binding to corticosteroid binding globulin. Budesonide rapidly equilibrated with red blood cells in a concentration independent manner with a blood plasma ratio of about 0.8.

Formoterol: Over the concentration range of 10-500 nmol/L, plasma protein binding for the RR and SS enantiomers of formoterol was 46% and 58%, respectively. The concentrations of formoterol used to assess the plasma protein binding were higher than those achieved in plasma following inhalation of a single 54 mcg dose.

Metabolism
Budesonide: In vitro studies with human liver homogenates have shown that budesonide was rapidly and extensively metabolized. Two major metabolites formed via cytochrome P450 (CYP) isoenzyme 3A4 (CYP3A4) catalyzed biotransformation have been isolated and identified as 16α-hydroxyprednisolone and 6ß-hydroxybudesonide. The corticosteroid activity of each of these two metabolites was less than 1% of that of the parent compound. No qualitative differences between the in vitro and in vivo metabolic patterns were detected. Negligible metabolic inactivation was observed in human lung and serum preparations.

Formoterol: The primary metabolism of formoterol is by direct glucuronidation and by O-demethylation followed by conjugation to inactive metabolites. Secondary metabolic pathways include deformylation and sulfate conjugation. CYP2D6 and CYP2C have been identified as being primarily responsible for O-demethylation.

Elimination
Budesonide: Budesonide was excreted in urine and feces in the form of metabolites. Approximately 60% of an intravenous radiolabeled dose was recovered in the urine.

No unchanged budesonide was detected in the urine. The 22R form of budesonide was preferentially cleared by the liver with systemic clearance of 1.4 L/min vs. 1.0 L/min for the 22S form. The terminal half-life, 2 to 3 hours, was the same for both epimers and was independent of dose.

Formoterol: The excretion of formoterol was studied in four healthy subjects following simultaneous administration of radiolabeled formoterol via the oral and IV routes. In that study, 62% of the radiolabeled formoterol was excreted in the urine while 24% was eliminated in the feces.

Special Populations

Geriatric

The pharmacokinetics of SYMBICORT in geriatric patients have not been specifically studied.

Pediatric

Plasma concentrations of budesonide were measured following administration of four inhalations of SYMBICORT 160/4.5 in a single-dose study in pediatric patients with asthma, 6 to less than 12 years of age. Peak budesonide concentrations of 1.4 nmol/L occurred at 20 minutes post-dose. This study also demonstrated that the total systemic exposure to budesonide from SYMBICORT was approximately 30% lower than from inhaled budesonide via a dry powder inhaler that was also evaluated at the same delivered dose. The dose-normalized Cmax and AUC0-inf of budesonide following single dose inhalation in children 6 to less than 12 years of age were numerically lower than that observed in adults.

Following 2 inhalations of SYMBICORT 160/4.5 twice daily treatment, formoterol Cmax and AUC0-6 at steady state in children 6 to less than 12 years of age were comparable to that observed in adults.

Gender/Race

Specific studies to examine the effects of gender and race on the pharmacokinetics of SYMBICORT have not been conducted. Population PK analysis of the SYMBICORT data indicates that gender does not affect the pharmacokinetics of budesonide and formoterol. No conclusions can be drawn on the effect of race due to the low number of non-Caucasians evaluated for PK.

Nursing Mothers

The disposition of budesonide when delivered by inhalation from a dry powder inhaler at doses of 200 or 400 mcg twice daily for at least 3 months was studied in eight lactating women with asthma from 1 to 6 months postpartum. Systemic exposure to budesonide in these women appears to be comparable to that in non-lactating women with asthma from other studies. Breast milk obtained over eight hours post-dose revealed that the maximum concentration of budesonide for the 400 and 800 mcg total daily doses was 0.39 and 0.78 nmol/L, respectively, and occurred within 45 minutes after dosing. The estimated oral daily dose of budesonide from breast milk to the infant is approximately 0.007 and 0.014 mcg/kg/day for the two dose regimens used in this study, which represents approximately 0.3% to 1% of the dose inhaled by the mother. Budesonide levels in plasma samples obtained from five infants at about 90 minutes after breastfeeding (and about 140 minutes after drug administration to the mother) were below quantifiable levels (<0.02 nmol/L in four infants and <0.04 nmol/L in one infant) [see Use in Specific Populations (8.2)].

Renal or Hepatic Insufficiency

There are no data regarding the specific use of SYMBICORT in patients with hepatic or renal impairment. Reduced liver function may affect the elimination of corticosteroids. Budesonide pharmacokinetics was affected by compromised liver function as evidenced by a doubled systemic availability after oral ingestion. The intravenous budesonide pharmacokinetics was, however, similar in cirrhotic patients and in healthy subjects. Specific data with formoterol is not available, but because formoterol is primarily eliminated via hepatic metabolism, an increased exposure can be expected in patients with severe liver impairment.

Drug-Drug Interactions

A single-dose crossover study was conducted to compare the pharmacokinetics of eight inhalations of the following: budesonide, formoterol, and budesonide plus formoterol administered concurrently. The results of the study indicated that there was no evidence of a pharmacokinetic interaction between the two components of SYMBICORT.

Inhibitors of Cytochrome P450 Enzymes

Ketoconazole: Ketoconazole, a strong inhibitor of cytochrome P450 (CYP) isoenzyme 3A4 (CYP3A4), the main metabolic enzyme for corticosteroids, increased plasma levels of orally ingested budesonide.

Cimetidine: At recommended doses, cimetidine, a non-specific inhibitor of CYP enzymes, had a slight but clinically insignificant effect on the pharmacokinetics of oral budesonide.

Specific drug-drug interaction studies with formoterol have not been performed.

13 NONCLINICAL TOXICOLOGY

13.1 Carcinogenesis, Mutagenesis, Impairment of Fertility

Budesonide

Long-term studies were conducted in rats and mice using oral administration to evaluate the carcinogenic potential of budesonide.

In a 2-year study in Sprague-Dawley rats, budesonide caused a statistically significant increase in the incidence of gliomas in male rats at an oral dose of 50 mcg/kg (approximately equivalent to the MRHDID in adults and children on a mcg/m^2 basis). No tumorigenicity was seen in male and female rats at respective oral doses up to 25 and 50 mcg/kg (approximately equivalent to the MRHDID in adults and children on a mcg/m^2 basis). In two additional 2-year studies in male Fischer and Sprague-Dawley rats, budesonide caused no gliomas at an oral dose of 50 mcg/kg (approximately equivalent to the MRHDID in adults and children on a mcg/m^2 basis). However, in the male Sprague-Dawley rats, budesonide caused a statistically significant increase in the incidence of hepatocellular tumors at an oral dose of 50 mcg/kg (approximately equivalent to the MRHDID in adults and children on a mcg/m^2 basis). The concurrent reference corticosteroids (prednisolone and triamcinolone acetonide) in these two studies showed similar findings.

In a 91-week study in mice, budesonide caused no treatment-related carcinogenicity at oral doses up to 200 mcg/kg (approximately 2 times the MRHDID in adults and children on a mcg/m^2 basis).

Budesonide was not mutagenic or clastogenic in six different test systems: Ames Salmonella/microsome plate test, mouse micronucleus test, mouse lymphoma test, chromosome aberration test in human lymphocytes, sex-linked recessive lethal test in Drosophila melanogaster, and DNA repair analysis in rat hepatocyte culture.

Fertility and reproductive performance were unaffected in rats at subcutaneous doses up to 80 mcg/kg (approximately equal to the MRHDID on a mcg/m^2 basis). However, it caused a decrease in prenatal viability and viability in the pups at birth and during lactation, along with a decrease in maternal body-weight gain, at subcutaneous doses of 20 mcg/kg and above (less than the MRHDID on a mcg/m^2 basis). No such effects were noted at 5 mcg/kg (less than the MRHDID on a mcg/m^2 basis).

Formoterol

Long-term studies were conducted in mice using oral administration and rats using inhalation administration to evaluate the carcinogenic potential of formoterol fumarate.

In a 24-month carcinogenicity study in CD-1 mice, formoterol at oral doses of 100 mcg/kg and above (approximately 30 and 15 times the MRHDID in adults and children, respectively, on a mcg/m^2 basis) caused a dose-related increase in the incidence of uterine leiomyomas.

In a 24-month carcinogenicity study in Sprague-Dawley rats, an increased incidence of mesovarian leiomyoma and uterine leiomyosarcoma were observed at the inhaled dose of 130 mcg/kg (approximately 70 and 35 times the MRHDID in adults and children, respectively, on a mcg/m^2 basis). No tumors were seen at 22 mcg/kg (approximately 12 and 6 times the MRHDID in adults and children, respectively, on a mcg/m^2 basis).

Other beta-agonist drugs have similarly demonstrated increases in leiomyomas of the genital tract in female rodents. The relevance of these findings to human use is unknown.

Formoterol was not mutagenic or clastogenic in Ames Salmonella/microsome plate test, mouse lymphoma test, chromosome aberration test in human lymphocytes, and rat micronucleus test.

A reduction in fertility and/or reproductive performance was identified in male rats treated with formoterol at an oral dose of 15,000 mcg/kg (approximately 2200 times the MRHDID on an AUC basis). No such effect was seen at 3000 mcg/kg (approximately 1600 times the MRHDID on a mcg/m^2 basis). In a separate study with male rats treated with an oral dose of 15,000 mcg/kg (approximately 8000 times the MRHDID on a mcg/m^2 basis), there were findings of testicular tubular atrophy and spermatic debris in the testes and oligospermia in the epididymides. No effect on fertility was detected in female rats at doses up to 15,000 mcg/kg (approximately 1100 times the MRHDID on an AUC basis).

13.2 Animal Toxicology and/or Pharmacology

Preclinical: Studies in laboratory animals (minipigs, rodents, and dogs) have demonstrated the occurrence of cardiac arrhythmias and sudden death (with histologic evidence of myocardial necrosis) when beta-agonists and methylxanthines are administered concurrently. The clinical significance of these findings is unknown.

14 CLINICAL STUDIES

14.1 Asthma

Patients with asthma 12 years of age and older

In two clinical studies comparing SYMBICORT with the individual components, improvements in most efficacy end points were greater with SYMBICORT than with the use of either budesonide or formoterol alone. In addition, one clinical study showed similar results between SYMBICORT and the concurrent use of budesonide and formoterol at corresponding doses from separate inhalers.

The safety and efficacy of SYMBICORT were demonstrated in two randomized, double-blind, placebo-controlled US clinical studies involving 1076 patients 12 years of age and older. Fixed SYMBICORT dosages of 160/9 mcg, and 320/9 mcg twice daily (each dose administered as 2 inhalations of the 80/4.5 and 160/4.5 mcg strengths, respectively) were compared with the monocomponents (budesonide and formoterol) and placebo to provide information about appropriate dosing to cover a range of asthma severity.

Study 1: Clinical Study with SYMBICORT 160/4.5

This 12-week study evaluated 596 patients 12 years of age and older by comparing SYMBICORT 160/4.5, the free combination of budesonide 160 mcg plus formoterol 4.5 mcg in separate inhalers, budesonide 160 mcg, formoterol 4.5 mcg, and placebo; each administered as 2 inhalations twice daily. The study included a 2-week run-in period with budesonide 80 mcg, 2 inhalations twice daily. Most patients had moderate to severe asthma and were using moderate to high doses of inhaled corticosteroids prior to study entry. Randomization was stratified by previous inhaled corticosteroid treatment (71.6% on moderate- and 28.4% on high-dose inhaled corticosteroid). Mean percent predicted FEV1 at baseline was 68.1% and was similar across treatment groups. The co-primary efficacy end points were 12-hour-average post-dose FEV1 at week 2, and pre-dose FEV1 averaged over the course of the study. The study also required that patients who satisfied a predefined asthma-worsening criterion be withdrawn. The predefined asthma-worsening criteria were a clinically important decrease in FEV1 or PEF, increase in rescue albuterol use, nighttime awakening due to asthma, emergency intervention or hospitalization due to asthma, or requirement for asthma medication not allowed by the protocol. For the criterion of nighttime awakening due to asthma, patients were allowed to remain in the study at the discretion of the investigator if none of the other asthma-worsening criteria were met. The percentage of patients withdrawing due to or meeting predefined criteria for worsening asthma is shown in Table 4.

Table 4 The number and percentage of patients withdrawing due to or meeting predefined criteria for worsening asthma (Study 1)
 | SYMBICORT 160/4.5; n = 124 | Budesonide; 160 mcg plus Formoterol; 4.5 mcg; n = 115 | Budesonide; 160 mcg; n = 109 | Formoterol; 4.5 mcg; n = 123 | Placebo; n = 125
Patients withdrawn due to predefined asthma event [These criteria were assessed on a daily basis irrespective of the timing of the clinic visit, with the exception of FEV1, which was assessed at each clinic visit.] | 13 (10.5) | 13 (11.3) | 22 (20.2) | 44 (35.8) | 62 (49.6)
Patients with a predefined asthma event, [Individual criteria are shown for patients meeting any predefined asthma event, regardless of withdrawal status.] | 37 (29.8) | 24 (20.9) | 48 (44.0) | 68 (55.3) | 84 (67.2)
Decrease in FEV1 | 4 (3.2) | 8 (7.0) | 7 (6.4) | 15 (12.2) | 14 (11.2)
Rescue medication use | 2 (1.6) | 0 | 3 (2.8) | 3 (2.4) | 7 (5.6)
Decrease in AM PEF | 2 (1.6) | 5 (4.3) | 5 (4.6) | 17 (13.8) | 15 (12.0)
Nighttime awakenings [For the criterion of nighttime awakening due to asthma, patients were allowed to remain in the study at the discretion of the investigator if none of the other criteria were met.] | 24 (19.4) | 11 (9.6) | 29 (26.6) | 32 (26.0) | 49 (39.2)
Clinical exacerbation | 7 (5.6) | 6 (5.2) | 5 (4.6) | 17 (13.8) | 16 (12.8)

Mean percent change from baseline in FEV1 measured immediately prior to dosing (pre-dose) over 12 weeks is displayed in Figure 1. Because this study used predefined withdrawal criteria for worsening asthma, which caused a differential withdrawal rate in the treatment groups, pre-dose FEV1 results at the last available study visit (end of treatment, EOT) are also provided. Patients receiving SYMBICORT 160/4.5 had significantly greater mean improvements from baseline in pre-dose FEV1 at the end of treatment (0.19 L, 9.4%), compared with budesonide 160 mcg (0.10 L, 4.9%), formoterol 4.5 mcg (-0.12 L, -4.8%), and placebo (-0.17 L, -6.9%).

Figure 1 Mean Percent Change From Baseline in Pre-dose FEV1 Over 12 Weeks (Study 1)

The effect of SYMBICORT 160/4.5 two inhalations twice daily on selected secondary efficacy variables, including morning and evening PEF, albuterol rescue use, and asthma symptoms over 24 hours on a 0-3 scale is shown in Table 5.

Table 5 Mean values for selected secondary efficacy variables (Study 1)
Efficacy Variable | SYMBICORT 160/4.5 (n [Number of patients (n) varies slightly due to the number of patients for whom data were available for each variable. Results shown are based on last available data for each variable.] =124) | Budesonide 160 mcg plus Formoterol 4.5 mcg (n=115) | Budesonide 160 mcg (n=109) | Formoterol 4.5 mcg (n=123) | Placebo (n=125)
AM PEF (L/min) Baseline | 341 | 338 | 342 | 339 | 355
Change from Baseline | 35 | 28 | 9 | -9 | -18
PM PEF (L/min) Baseline | 351 | 348 | 357 | 354 | 369
Change from Baseline | 34 | 26 | 7 | -7 | -18
Albuterol rescue use; Baseline | 2.1 | 2.3 | 2.7 | .5 | 2.4
Change from Baseline | -1.0 | -1.5 | -0.8 | -0.3 | 0.8
Average symptom score/day (0–3 scale); Baseline | 0.99 | 1.03 | 1.04 | 1.04 | 1.08
Change from Baseline | -0.28 | -0.32 | -0.14 | -0.05 | 0.10

The subjective impact of asthma on patients’ health-related quality of life was evaluated through the use of the standardized Asthma Quality of Life Questionnaire (AQLQ(S)) (based on a 7-point scale where 1 = maximum impairment and 7 = no impairment). Patients receiving SYMBICORT 160/4.5 had clinically meaningful improvement in overall asthma-specific quality of life, as defined by a mean difference between treatment groups of >0.5 points in change from baseline in overall AQLQ score (difference in AQLQ score of 0.70 [95% CI 0.47, 0.93], compared to placebo).

Study 2: Clinical Study with SYMBICORT 80/4.5

This 12-week study was similar in design to Study 1, and included 480 patients 12 years of age and older. This study compared SYMBICORT 80/4.5, budesonide 80 mcg, formoterol 4.5 mcg, and placebo; each administered as 2 inhalations twice daily. The study included a 2-week placebo run-in period. Most patients had mild to moderate asthma and were using low to moderate doses of inhaled corticosteroids prior to study entry. Mean percent predicted FEV1 at baseline was 71.3% and was similar across treatment groups. Efficacy variables and end points were identical to those in Study 1.

The percentage of patients withdrawing due to or meeting predefined criteria for worsening asthma is shown in Table 6. The method of assessment and criteria used were identical to that in Study 1.

Table 6 The number and percentage of patients withdrawing due to or meeting predefined criteria for worsening asthma (Study 2)
 | SYMBICORT; 80/4.5; (n=123) | Budesonide; 80 mcg; (n=121) | Formoterol; 4.5 mcg; (n=114) | Placebo; (n=122)
Patients withdrawn due to predefined asthma event [These criteria were assessed on a daily basis irrespective of the timing of the clinic visit, with the exception of FEV1, which was assessed at each clinic visit.] | 9 (7.3) | 8 (6.6) | 21 (18.4) | 40 (32.8)
Patients with a predefined asthma event, [Individual criteria are shown for patients meeting any predefined asthma event, regardless of withdrawal status.] | 23 (18.7) | 26 (21.5) | 48 (42.1) | 69 (56.6)
Decrease in FEV1 | 3 (2.4) | 3 (2.5) | 11 (9.6) | 9 (7.4)
Rescue medication use | 1 (0.8) | 3 (2.5) | 1 (0.9) | 3 (2.5)
Decrease in AM PEF | 3 (2.4) | 1 (0.8) | 8 (7.0) | 14 (11.5)
Nighttime awakening [For the criterion of nighttime awakening due to asthma, patients were allowed to remain in the study at the discretion of the investigator if none of the other criteria were met.] | 17 (13.8) | 20 (16.5) | 31 (27.2) | 52 (42.6)
Clinical exacerbation | 1 (0.8) | 3 (2.5) | 5 (4.4) | 20 (16.4)

Mean percent change from baseline in pre-dose FEV1 over 12 weeks is displayed in Figure 2.

Figure 2 Mean Percent Change From Baseline in Pre-dose FEV1 Over 12 Weeks (Study 2)

Efficacy results for other secondary end points, including quality of life, were similar to those observed in Study 1.

Onset and Duration of Action and Progression of Improvement in Asthma Control

The onset of action and progression of improvement in asthma control were evaluated in the two pivotal clinical studies. The median time to onset of clinically significant bronchodilation (>15% improvement in FEV1) was seen within 15 minutes. Maximum improvement in FEV1 occurred within 3 hours, and clinically significant improvement was maintained over 12 hours. Figures 3 and 4 show the percent change from baseline in post-dose FEV1 over 12 hours on the day of randomization and on the last day of treatment for Study 1.

Reduction in asthma symptoms and in albuterol rescue use, as well as improvement in morning and evening PEF, occurred within 1 day of the first dose of SYMBICORT; improvement in these variables was maintained over the 12 weeks of therapy.

Following the initial dose of SYMBICORT, FEV1 improved markedly during the first 2 weeks of treatment, continued to show improvement at the Week 6 assessment, and was maintained through Week 12 for both studies.

No diminution in the 12-hour bronchodilator effect was observed with either SYMBICORT 80/4.5 or SYMBICORT 160/4.5, as assessed by FEV1, following 12 weeks of therapy or at the last available visit.

FEV1 data from Study 1 evaluating SYMBICORT 160/4.5 is displayed in Figures 3 and 4.

Figure 3 Mean Percent Change From Baseline in FEV1 on Day of Randomization (Study 1)

Figure 4 Mean Percent Change From Baseline in FEV1 at End of Treatment (Study 1)

Patients with asthma 6 to less than 12 years of age

The clinical program to support the efficacy of SYMBICORT 80/4.5 in children 6 to less than 12 years of age included the following: 1) a budesonide dose confirmatory study, 2) a formoterol dose finding study, and 3) an efficacy and safety study of the SYMBICORT combination product.

The selection of budesonide 80 mcg is supported by a 6-week, randomized, double-blind, placebo-controlled study in 304 pediatric patients (152 budesonide, 152 placebo) 6 to less than 12 years of age with asthma. Results showed that budesonide 80 mcg (2 inhalations twice daily) provided statistically significantly greater improvement compared to placebo for the primary endpoint of change from baseline to the treatment period average in pre-dose morning PEF and the key secondary endpoint of change in pre-dose morning FEV1. The selection of the formoterol dose is supported by a randomized, single dose, placebo-controlled, active-controlled (Foradil Aerolizer 12 mcg), 5-way cross-over study in which doses of 2.25, 4.5 and 9 mcg formoterol were administered in combination with budesonide in 54 pediatric patients 6 to less than 12 years of age with asthma. Results showed a dose response of formoterol compared to placebo for the primary endpoint of FEV1 averaged over 12 hours post-dose and the 9 mcg group showed numerically similar results compared to the active control.

The confirmatory efficacy study was a 12-week, randomized, double-blind, multicenter study in which SYMBICORT 80/4.5 was compared with budesonide pMDI 80 mcg, each administered as 2 inhalations twice daily, in 184 pediatric patients 6 to less than 12 years of age with a documented clinical diagnosis of asthma. At trial entry, the children had a requirement for daily medium-dose range inhaled corticosteroid therapy or fixed combination of inhaled corticosteroid and LABA therapy, and exhibited symptoms despite treatment with a low-dose inhaled corticosteroid during a 2 to 4 week run-in period. The primary efficacy variable was change from baseline to Week 12 in clinic-measured 1-hour post-dose FEV1. In patients receiving SYMBICORT 80/4.5, there was a statistically significant change compared to budesonide in 1-hour post-dose FEV1 which improved by 0.28 L from baseline to Week 12, as compared with 0.17 L for those receiving budesonide 80 mcg (mean difference 0.12 L; 95% CI: 0.03, 0.20) (see Figure 5).

Figure 5 Change From Baseline in Clinic-Measured 1-hour Post-dose FEV1 over 12 Weeks (Efficacy and Safety Study in Patients 6 to less than 12 years of age).

Similarly, improvement was noted in change from baseline to Week 12 for 1-hour post-dose clinic PEF (mean difference 25.5 L/min; 95% CI: 10.9, 40.0). Bronchodilatory effects were evident from the first assessment at 15 minutes on day 1 and were maintained at Week 12. The estimated mean difference between SYMBICORT 80/4.5 and budesonide with respect to change from baseline to Week 12 in 15 minutes post-dose clinic FEV1 was 0.10 L (95% CI: 0.02, 0.18). No differences between SYMBICORT and budesonide were noted in nighttime awakenings, rescue albuterol use, or Pediatric Asthma Quality of Life Questionnaire (PAQLQ) scores. The proportion of patients with at least 0.5 points improvement from baseline to Week 12 in PAQLQ was 42% on SYMBICORT 80/4.5 and 46% on budesonide 80 mcg.

Postmarketing Safety and Efficacy Study

A randomized, double-blind, parallel-group, safety study compared SYMBICORT with budesonide, each administered as 2 inhalations twice daily over 26 weeks (NCT01444430). The primary safety objective was to evaluate whether the addition of formoterol to budesonide therapy (SYMBICORT) was non-inferior to budesonide in terms of the risk of serious asthma-related events (asthma-related hospitalization, endotracheal intubation, and death). The study was designed to rule out a pre-defined risk margin of serious asthma-related events of 2.0. A blinded adjudication committee determined whether events were asthma-related.

This study enrolled patients who were 12 years of age and older, had a clinical diagnosis of asthma for at least 1 year, and had at least 1 asthma exacerbation requiring treatment with systemic corticosteroids or an asthma-related hospitalization in the previous year. Patients were stratified to one of the two dose levels of SYMBICORT or budesonide based on assessment of asthma control and ongoing asthma therapy. Patients with a history of life-threatening asthma were excluded. The study included 11,693 patients [5846 receiving SYMBICORT (80/4.5 or 160/4.5) and 5847 receiving budesonide (80 or 160 mcg)], whose mean age was 44 years, and of whom 66% were female and 69% were Caucasian.

SYMBICORT was non-inferior to budesonide in terms of time to first serious asthma-related events based on the pre-specified risk margin, with an estimated hazard ratio of 1.07 [95% CI: 0.70, 1.65] (Table 7).

Table 7 Serious Asthma-Related Events (Postmarketing Safety and Efficacy study)
 | SYMBICORT (N [N = total number of patients] =5846); n [n = number of patients with the event] (%) | Budesonide (N=5847); n (%) | SYMBICORT vs. Budesonide Hazard ratio (95% CI) [The hazard ratio for time to first event was based on a non-stratified Cox proportional hazard model with covariates of treatment (SYMBICORT vs. budesonide) and inhaled corticosteroid dose level (160 mcg vs. 80 mcg), as randomized. If the resulting upper 95% CI estimate for the relative risk was < 2.0, then non-inferiority was concluded.]
Serious asthma-related event [Asthma-related hospitalization, endotracheal intubation, or death that occurred within 6 months after the first use of study drug or 7 days after the last date of study drug, whichever date was later. Patients can have one or more events, but only the first event was counted for analysis. A single, blinded, independent adjudication committee determined whether events were asthma-related.] | 43 (0.7) | 40 (0.7) | 1.07 (0.70, 1.65)
Asthma-related death | 2 (<0.1) | 0
Asthma-related endotracheal intubation | 1 (<0.1) | 0
Asthma-related hospitalization | 42 (0.7) | 40 (0.7)

The primary efficacy endpoint was asthma exacerbations, defined as a deterioration of asthma that led to use of systemic corticosteroids for at least 3 days, or a hospitalization, or an emergency room visit that required systemic corticosteroids. The estimated hazard ratio for time to first asthma exacerbation rate for SYMBICORT relative to budesonide was 0.84 [95% CI: 0.75, 0.94]. This outcome was primarily driven by a reduction in systemic corticosteroid use.

14.2 Chronic Obstructive Pulmonary Disease

Lung Function

The efficacy of SYMBICORT 80/4.5 and SYMBICORT 160/4.5 in the maintenance treatment of airflow obstruction in COPD patients was evaluated in two randomized, double-blind, placebo-controlled multinational studies, conducted over 6 months (Study 1) and 12 months (Study 2), in a total of 3668 patients (2416 males and 1252 females). The majority of patients (93%) were Caucasian. All patients were required to be at least 40 years of age, with a FEV1 of less than or equal to 50% predicted, a clinical diagnosis of COPD with symptoms for at least 2 years, and a smoking history of at least 10 pack years, prior to entering the trial. The mean prebronchodilator FEV1 at baseline of the patients enrolled in the study was 34% predicted. Forty-eight percent of the patients enrolled were on inhaled corticosteroids and 52.7% of patients were on short-acting anticholinergic bronchodilators during run-in. On randomization, inhaled corticosteroids were discontinued, and ipratropium bromide was allowed at a stable dose for those patients previously treated with short-acting anticholinergic bronchodilators. The co-primary efficacy variables in both studies were the change from baseline in average pre-dose and 1-hour post-dose FEV1 over the treatment period. The results of both studies 1 and 2 are described below.

Study 1

This was a 6-month, placebo-controlled study of 1704 COPD patients (mean % predicted FEV1 at baseline ranging from 33.5% -34.7%) conducted to demonstrate the efficacy and safety of SYMBICORT in the treatment of airflow obstruction in COPD. The patients were randomized to one of the following treatment groups: SYMBICORT 160/4.5 (n=277), SYMBICORT 80/4.5 (n=281), budesonide 160 mcg + formoterol 4.5 mcg (n=287), budesonide 160 mcg (n=275), formoterol 4.5 mcg (n=284), or placebo (n=300). Patients receiving SYMBICORT 160/4.5, two inhalations twice daily, had significantly greater mean improvements from baseline in pre-dose FEV1 averaged over the treatment period [0.08 L, 10.7%] compared with formoterol 4.5 mcg [0.04 L, 6.9%] and placebo [0.01 L, 2.2%] (see Figure 6). Patients receiving SYMBICORT 80/4.5, two inhalations twice daily, did not have significantly greater improvement from baseline in the pre-dose FEV1 averaged over the treatment period compared with formoterol 4.5 mcg.

Figure 6 Mean Percent Change From Baseline in Pre-dose FEV1 over 6 Months (Study 1)

Patients receiving SYMBICORT 160/4.5, two inhalations twice daily, had significantly greater mean improvements from baseline in 1-hour post-dose FEV1 averaged over the treatment period [0.20 L, 22.6%], compared with budesonide 160 mcg [0.03 L, 4.9%] and placebo [0.03 L, 4.1%] (see Figure 7).

Figure 7 Mean Percent Change From Baseline in 1-hour Post-dose FEV1 Over 6 months (Study 1)

Study 2

This was a 12-month, placebo-controlled study of 1964 COPD patients (mean % predicted FEV1 at baseline ranging from 33.7% -35.5%) conducted to demonstrate the efficacy and safety of SYMBICORT in the treatment of airflow obstruction in COPD. The patients were randomized to one of the following treatment groups: SYMBICORT 160/4.5 (n=494), SYMBICORT 80/4.5 (n=494), formoterol 4.5 mcg (n=495), or placebo (n=481). Patients receiving SYMBICORT 160/4.5, two inhalations twice daily, had significantly greater improvements from baseline in mean pre-dose FEV1 averaged over the treatment period [0.10 L, 10.8%] compared with formoterol 4.5 mcg [0.06 L, 7.2%] and placebo [0.01 L, 2.8%]. Patients receiving SYMBICORT 80/4.5, two inhalations twice daily, did not have significantly greater improvements from baseline in the mean pre-dose FEV1 averaged over the treatment period compared to formoterol. Patients receiving SYMBICORT 160/4.5, two inhalations twice daily, also had significantly greater mean improvements from baseline in 1-hour post-dose FEV1 averaged over the treatment period [0.21 L, 24.0%] compared with placebo [0.02 L, 5.2%].

Serial FEV1 measures over 12 hours were obtained in a subset of patients in Study 1 (n=99) and Study 2 (n=121). The median time to onset of bronchodilation, defined as an FEV1 increase of 15% or greater from baseline, occurred at 5 minutes post-dose. Maximum improvement (calculated as the average change from baseline at each timepoint) in FEV1 occurred at approximately 2 hours post-dose.

In both Studies 1 and 2, improvements in secondary endpoints of morning and evening peak expiratory flow and reduction in rescue medication use were supportive of the efficacy of SYMBICORT 160/4.5.

Exacerbations

Studies 3 and 4 were primarily designed to evaluate the effect of SYMBICORT 160/4.5 on COPD exacerbations.

Study 3

This was a 6-month, active-control study conducted to evaluate the effect of SYMBICORT 160/4.5 compared to formoterol 4.5 mcg, each administered as 2 inhalations twice daily, on the rate of moderate and severe COPD exacerbations. COPD exacerbations were defined as worsening of 2 or more major symptoms (dyspnea, sputum volume, sputum color/purulence) or worsening of any 1 major symptom together with at least 1 of the minor symptoms: sore throat, colds (nasal discharge and/or nasal congestion), fever without other cause, increased cough or increased wheeze for at least 2 consecutive days. COPD exacerbations were considered of moderate severity if treatment of symptoms with systemic corticosteroids (≥3 days) and/or antibiotics were required, and were considered severe if hospitalization was required. The study randomized 1219 subjects to SYMBICORT 160/4.5 (606) and formoterol 4.5 mcg (613) of which 57% were male and 92% were Caucasian. They had a mean age of 64 years and a median smoking history of 39 pack years, with 46% identified as current smokers. At run-in, the mean post-bronchodilator % predicted normal FEV1 was 48.7% (range: 16.0% to 78.1%), and patients had a history of at least 1 COPD exacerbation in the previous year treated with systemic corticosteroids and/or hospitalization. All subjects were treated with SYMBICORT 160/4.5, two inhalations twice daily during a 4-week run-in period prior to being assigned trial treatment.

Study 4

This was a 12-month, active-control study which included 811 subjects treated with SYMBICORT 160/4.5 or formoterol 4.5 mcg, each administered as 2 inhalations twice daily. The study was conducted to evaluate for COPD exacerbation reduction in patients with COPD. COPD exacerbations were defined as worsening of COPD that required a course of oral steroids for treatment and/or hospitalization. This study randomized 407 subjects to SYMBICORT 160/4.5 and 404 to formoterol 4.5 mcg of which 61% were male and 83% were Caucasian. They had a mean age of 63 years and a median smoking history of 45 pack years, with 36% identified as current smokers. At run-in, the mean post-bronchodilator % predicted normal FEV1 was 37.8% (range: 11.75% to 76.50%), and a history of at least 1 COPD exacerbation in the previous year treated with systemic corticosteroids and/or antibiotics.

In Study 3, subjects treated with SYMBICORT 160/4.5, two inhalations twice daily had a significantly lower annual rate of moderate/severe COPD exacerbations compared with formoterol 4.5 mcg with a reduction of 26% (95% CI: 9%, 39%). In Study 4, a significantly lower annual rate of exacerbations was also observed in subjects treated with SYMBICORT 160/4.5 compared with formoterol 4.5 mcg with a reduction of 35% (95% CI: 20%, 47%) (Table 8).

Table 8 Chronic Obstructive Pulmonary Disease Exacerbations
 | n | Annual Rate Estimate | Rate ratio Symbicort 160/4.5 vs. Formoterol 4.5 mcg
Treatment |  |  | Estimate | 95% CI
Study 3
SYMBICORT 160/4.5 | 606 | 0.94 | 0.74 | 0.61, 0.91
Formoterol 4.5 mcg | 613 | 1.27
Study 4
SYMBICORT 160/4.5 | 404 | 0.68 | 0.65 | 0.53, 0.80
Formoterol 4.5 mcg | 403 | 1.05

n – Number of patients included in efficacy analysis set.

Health-related quality of life was measured using the St. George’s Respiratory Questionnaire (SGRQ) in both COPD exacerbation clinical studies.

In Study 3, the SGRQ responder rates at 6-months (defined as an improvement in score of 4 or more as a threshold) were 40% and 33% for SYMBICORT 160/4.5 and formoterol 4.5 mcg, respectively, with an odds ratio of 1.5 (95% CI: 1.0, 2.0) for SYMBICORT 160/4.5 vs. formoterol 4.5 mcg. In Study 4, the responder rates at 12-months were 50% and 49% for SYMBICORT 160/4.5 and formoterol 4.5 mcg, respectively, with an odds ratio of 1.0 (95% CI: 0.8, 1,4) for SYMBICORT 160/4.5 vs. formoterol 4.5 mcg.

16 HOW SUPPLIED/STORAGE AND HANDLING

Product: 50090-1403

NDC: 50090-1403-0 1 AEROSOL in a POUCH / 1 in a CARTON

17 PATIENT COUNSELING INFORMATION

Advise the patient to read the FDA-approved patient labeling (Patient Information and Instructions for Use).

Serious Asthma-Related Events: Inform patients with asthma that LABA when used alone increases the risk of asthma-related hospitalization or asthma-related death. Available data show that when ICS and LABA are used together, such as with SYMBICORT, there is not a significant increase in risk of these events.

Not for Acute Symptoms: Inform patients that SYMBICORT is not meant to relieve acute symptoms of asthma or COPD and extra doses should not be used for that purpose. Advise patients to treat acute symptoms with an inhaled, short-acting beta2-agonist such as albuterol. Provide patients with such medication and instruct the patient in how it should be used.

Instruct patients to seek medical attention immediately if they experience any of the following:

• Decreasing effectiveness of inhaled, short-acting beta 2 -agonists
• Need for more inhalations than usual of inhaled, short-acting beta 2 -agonists
• Significant decrease in lung function as outlined by the physician

Tell patients they should not stop therapy with SYMBICORT without physician/provider guidance since symptoms may recur after discontinuation.

Do Not Use Additional Long-Acting Beta2-Agonists: Instruct patients not to use other LABA for asthma and COPD.

Local Effects: Inform patients that localized infections with Candida albicans occurred in the mouth and pharynx in some patients. If oropharyngeal candidiasis develops, it should be treated with appropriate local or systemic (i.e., oral) antifungal therapy while still continuing therapy with SYMBICORT, but at times therapy with SYMBICORT may need to be temporarily interrupted under close medical supervision. Rinsing the mouth with water without swallowing after inhalation is advised to reduce the risk of thrush.

Pneumonia: Patients with COPD have a higher risk of pneumonia; instruct them to contact their healthcare provider if they develop symptoms of pneumonia.

Immunosuppression: Warn patients who are on immunosuppressant doses of corticosteroids to avoid exposure to chicken pox or measles and, if exposed, to consult their physician without delay. Inform patients of potential worsening of existing tuberculosis, fungal, bacterial, viral, or parasitic infections, or ocular herpes simplex.

Hypercorticism and Adrenal Suppression: Advise patients that SYMBICORT may cause systemic corticosteroid effects of hypercorticism and adrenal suppression. Additionally, inform patients that deaths due to adrenal insufficiency have occurred during and after transfer from systemic corticosteroids. Patients should taper slowly from systemic corticosteroids if transferring to SYMBICORT.

Reduction in Bone Mineral Density: Advise patients who are at an increased risk for decreased BMD that the use of corticosteroids may pose an additional risk.

Reduced Growth Velocity: Inform patients that orally inhaled corticosteroids, a component of SYMBICORT, may cause a reduction in growth velocity when administered to pediatric patients. Physicians should closely follow the growth of children and adolescents taking corticosteroids by any route.

Ocular Effects: Long-term use of inhaled corticosteroids may increase the risk of some eye problems (cataracts or glaucoma); consider regular eye examinations.

Risks Associated With Beta-Agonist Therapy: Inform patients of adverse effects associated with beta2-agonists, such as palpitations, chest pain, rapid heart rate, tremor, or nervousness.

SYMBICORT is a trademark of the AstraZeneca group of companies.

©AstraZeneca 2017

Manufactured for: AstraZeneca Pharmaceuticals LP, Wilmington, DE 19850

By: AstraZeneca Dunkerque Production, Dunkerque, France

Product of France

Patient Information

SYMBICORT (SIM-bi-kort)
(budesonide 80 mcg and formoterol fumarate dihydrate 4.5 mcg)

Inhalation Aerosol

SYMBICORT (SIM-bi-kort)
(budesonide 160 mcg and formoterol fumarate dihydrate 4.5 mcg)

Inhalation Aerosol

What is SYMBICORT?

SYMBICORT combines an inhaled corticosteroid medicine (ICS), budesonide and a long-acting beta2-adrenergic agonist (LABA) medicine, formoterol.

- Inhaled corticosteroids help to decrease inflammation in the lungs. Inflammation in the lungs can lead to breathing problems.
- LABA medicines are used in people with chronic obstructive pulmonary disease (COPD) and asthma. LABA medicines help the muscles around the airways in your lungs stay relaxed to prevent symptoms such as wheezing, cough, chest tightness, and shortness of breath. These symptoms can happen when the muscles around the airways tighten. This makes it hard to breathe. In severe cases, wheezing can stop your breathing and may lead to death if not treated right away.

SYMBICORT is not used to relieve sudden breathing problems and will not replace a rescue inhaler.

SYMBICORT is used for asthma and COPD as follows:

- Asthma: SYMBICORT is used to control symptoms of asthma, and prevent symptoms such as wheezing in adults and children ages 6 and older.
  SYMBICORT contains formoterol. LABA medicines such as formoterol when used alone increase the risk of death and hospitalizations from asthma problems. SYMBICORT contains an ICS and a LABA. When an ICS and LABA are used together, there is not a significant increased risk in hospitalizations and death from asthma problems. SYMBICORT is not for adults and children with asthma who are well controlled with an asthma-control medicine, such as a low to medium dose of an ICS. SYMBICORT is for adults and children with asthma who need both an ICS and LABA medicine.
  It is not known if SYMBICORT is safe and effective in children less than 6 years of age with asthma.
- COPD: COPD is a long-term (chronic) lung disease that includes chronic bronchitis, emphysema, or both. SYMBICORT 160/4.5 mcg is used long-term, as 2 inhalations 2 times each day, to improve symptoms of COPD for better breathing and to reduce the number of flare-ups (the worsening of your COPD symptoms for several days).

Do not use SYMBICORT:

- to treat sudden severe symptoms of asthma or COPD.
- if you are allergic to any of the ingredients in SYMBICORT. See the end of this leaflet for a list of ingredients in SYMBICORT.

Before you use SYMBICORT, tell your healthcare provider about all of your medical conditions, including if you:

- have heart problems.
- have high blood pressure.
- have seizures.
- have thyroid problems.
- have diabetes.
- have liver problems.
- have osteoporosis.
- have an immune system problem.
- have eye problems such as increased pressure in the eye, glaucoma, or cataracts.
- are allergic to any medicines.
- have any type of viral, bacterial, fungal, or parasitic infection.
- are exposed to chicken pox or measles.
- are pregnant or plan to become pregnant. It is not known if SYMBICORT may harm your unborn baby.
- are breastfeeding. Budesonide, one of the active ingredients in SYMBICORT, passes into breast milk. You and your healthcare provider should decide if you will take SYMBICORT while breast-feeding.

Tell your healthcare provider about all the medicines you take including prescription and over-the-counter medicines, vitamins, and herbal supplements. SYMBICORT and certain other medicines may interact with each other. This may cause serious side effects. Especially tell your healthcare provider if you take antifungal or anti-HIV medicines.

Know all the medicines you take. Keep a list and show it to your healthcare provider and pharmacist each time you get a new medicine.

How should I use SYMBICORT?

See the step-by-step instructions for using SYMBICORT at the end of this Patient Information leaflet. Do not use SYMBICORT unless your healthcare provider has taught you and you understand everything. Ask your healthcare provider or pharmacist if you have any questions.

- Use SYMBICORT exactly as prescribed. Do not use SYMBICORT more often than prescribed. SYMBICORT comes in 2 strengths. Your healthcare provider has prescribed the strength that is best for you. Note the differences between SYMBICORT and your other inhaled medications, including the differences in prescribed use and physical appearance.
- Children should use SYMBICORT with an adult’s help, as instructed by the child’s healthcare provider.
- SYMBICORT should be taken every day as 2 puffs in the morning and 2 puffs in the evening about 12 hours apart.
- If you miss a dose of SYMBICORT, you should take your next dose at the same time you normally do.
- Rinse your mouth with water and spit the water out after each dose (2 puffs) of SYMBICORT. Do not swallow the water. This will help to lessen the chance of getting a fungus infection (thrush) in the mouth and throat.
- If you take too much SYMBICORT, call your healthcare provider or go to the nearest hospital emergency room right away if you have any unusual symptoms, such as worsening shortness of breath, chest pain, increased heart rate, or shakiness.
- Do not spray SYMBICORT in your eyes. If you accidentally get SYMBICORT in your eyes, rinse your eyes with water, and if redness or irritation persists, consult your healthcare provider.
- Do not change or stop any medicines used to control or treat your breathing problems. Your healthcare provider will change your medicines as needed.
- While you are using SYMBICORT 2 times each day, do not use other medicines that contain a LABA for any reason. Ask your healthcare provider or pharmacist if any of your other medicines are LABA medicines.
- SYMBICORT does not relieve sudden symptoms. Always have a rescue inhaler medicine with you to treat sudden symptoms. If you do not have a rescue inhaler, call your healthcare provider to have one prescribed for you.
- Call your healthcare provider or get medical care right away if:
  ∘ your breathing problems worsen with SYMBICORT.
  ∘ you need to use your rescue inhaler medicine more often than usual.
  ∘ your rescue inhaler medicine does not work as well for you at relieving symptoms.
  ∘ your peak flow meter results decrease. Your healthcare provider will tell you the numbers that are right for you.
  ∘ your symptoms do not improve after using SYMBICORT regularly for 1 week.

What are the possible side effects of SYMBICORT?

SYMBICORT may cause serious side effects, including:

  ∘ chest pain
  ∘ a fast and irregular heartbeat
  ∘ tremor

∘ increased blood pressure
∘ headache
∘ nervousness

- Fungal infection in your mouth or throat (thrush). Rinse your mouth with water without swallowing after using SYMBICORT to help reduce your chance of getting thrush.
- Pneumonia and other lower respiratory tract infections. People with COPD have a higher chance of getting pneumonia and other lung infections. Inhaled corticosteroids may increase the chance of getting pneumonia. Call your healthcare provider if you notice any of these symptoms:

  ∘ increase in mucus (sputum) production
  ∘ fever
  ∘ increased cough

∘ change in mucus color
∘ chills
∘ increased breathing problems

- Immune system effects and a higher chance for infections. Tell your healthcare provider about any signs of infection such as:

  ∘ fever
  ∘ body aches
  ∘ feeling tired
  ∘ vomiting

∘ pain
∘ chills
∘ nausea

- Adrenal insufficiency. Adrenal insufficiency is a condition in which the adrenal glands do not make enough steroid hormones. This can happen when you stop taking oral corticosteroid medicines and start inhaled corticosteroid medicine.
- Increased wheezing right after taking SYMBICORT. Always have a rescue inhaler with you to treat sudden wheezing.
- Serious allergic reactions including rash, hives, swelling of the face, mouth, and tongue, and breathing problems. Call your healthcare provider or get emergency medical care if you get any symptoms of a serious allergic reaction.
- Lower bone mineral density. This can happen in people who have a high chance for low bone mineral density (osteoporosis). Your healthcare provider should check you for this during treatment with SYMBICORT.
- Slowed growth in children. A child’s growth should be checked regularly while using SYMBICORT.
- Eye problems including glaucoma and cataracts. You should have regular eye exams while using SYMBICORT.
- Swelling of your blood vessels. This can happen in people with asthma. Tell your healthcare provider right away if you have:

  ∘ a feeling of pins and needles or numbness of your arms or legs
  ∘ rash

∘ flu like symptoms
∘ pain and swelling of the sinuses

- Decreases in blood potassium levels (hypokalemia).
- Increases in blood sugar levels (hyperglycemia).

The most common side effects of SYMBICORT include:

People with asthma:

- throat irritation
- upper respiratory tract infection
- inflammation of mucous membranes of the sinuses (sinusitis)
- back pain
- stomach discomfort
- thrush in the mouth and throat. Rinse your mouth with water without swallowing after use to help prevent thrush

- headache
- throat pain
- flu
- nasal congestion
- vomiting

People with COPD:

- throat irritation.
- thrush in the mouth and throat. Rinse your mouth with water without swallowing after use to help prevent thrush.
- infection and inflammation of the mucous membranes of the bronchial tubes (bronchitis).
- inflammation of mucous membranes in the sinuses (sinusitis).
- upper respiratory tract infection.

Tell your healthcare provider about any side effect that bothers you or that does not go away.

These are not all the possible side effects of SYMBICORT.

Call your doctor for medical advice about side effects. You may report side effects to FDA at 1-800-FDA-1088.

You may also report side effects to AstraZeneca at 1-800-236-9933.

How should I store SYMBICORT?

- Store SYMBICORT at room temperature between 68°F to 77°F (20°C to 25°C).
- Store SYMBICORT with the mouthpiece down.
- The contents of your SYMBICORT canister are under pressure. Do not puncture or throw the canister into a fire or incinerator. Do not use or store it near heat or open flame. Storage above 120ºF may cause the canister to burst.
- Throw away SYMBICORT when the counter reaches zero (“0”) or 3 months after you take SYMBICORT out of its foil pouch, whichever comes first.
- Keep SYMBICORT and all medicines out of the reach of children.

General Information about the safe and effective use of SYMBICORT.

Medicines are sometimes prescribed for purposes other than those listed in a Patient Information leaflet. Do not use SYMBICORT for a condition for which it was not prescribed. Do not give SYMBICORT to other people, even if they have the same symptoms that you have. It may harm them.

You can ask your healthcare provider or pharmacist for information about SYMBICORT that is written for health professionals.

What are the ingredients in SYMBICORT?

Active ingredients: micronized budesonide and micronized formoterol fumarate dihydrate
Inactive ingredients: hydrofluroalkane (HFA 227), povidone K25 USP, and polyethylene glycol 1000 NF

Manufactured for: AstraZeneca Pharmaceuticals LP, Wilmington, DE 19850

By: AstraZeneca Dunkerque Production, Dunkerque, France Product of France

For more information, call 1-800-236-9933 or go to www.MySymbicort.com.

Revised: December 2017

Instructions for Use

SYMBICORT (SIM-bi-kort)

(budesonide 80 mcg and formoterol fumarate dihydrate 4.5 mcg)

Inhalation Aerosol

SYMBICORT (SIM-bi-kort)

(budesonide 160 mcg and formoterol fumarate dihydrate 4.5 mcg)

Inhalation Aerosol

Upright Position

How to Use SYMBICORT

Follow the instructions below for using SYMBICORT. You will breathe-in (inhale) the medicine. If you have any questions, ask your doctor or pharmacist.

Preparing your SYMBICORT inhaler for use

1. Take your SYMBICORT out of the moisture-protective foil pouch before you use it for the first time and throw the foil away. Write the date that you open the foil pouch on the box.
2. A counter is attached to the top of the metal canister. The counter will count down each time you release a puff of SYMBICORT. The arrow points to the number of inhalations (puffs) left in the canister. The counter will stop counting at zero (“0”).
3. Use the SYMBICORT canister only with the red SYMBICORT inhaler supplied with the product. Parts of the SYMBICORT inhaler should not be used with parts from any other inhalation product.
4. Shake your SYMBICORT inhaler well for 5 seconds right before each use. Remove the mouthpiece cover by squeezing gently at both sides, then pulling out (see Figure 2). Check the mouthpiece for foreign objects before use.

5. Priming your SYMBICORT inhaler
  Before you use SYMBICORT for the first time, you will need to prime it. To prime SYMBICORT, hold it in the upright position. See Figure 1. Shake the SYMBICORT inhaler well for 5 seconds. Hold your SYMBICORT inhaler facing away from you and press down firmly and fully on the top of the counter on the SYMBICORT inhaler to release a test spray. Then shake it again for 5 seconds and release a second test spray. Your SYMBICORT inhaler is now primed and ready for use. After you have primed the SYMBICORT inhaler for the first time, the counter will read either 120 or 60, depending on which size was provided to you.

If you do not use your SYMBICORT inhaler for more than 7 days or if you drop it, you will need to prime again.

Ways to hold the SYMBICORT inhaler for use

OR

Using your SYMBICORT inhaler

6. Shake your SYMBICORT inhaler well for 5 seconds. Remove the mouthpiece cover. Check the mouthpiece for foreign objects.
7. Breathe out fully (exhale). Hold the SYMBICORT inhaler up to your mouth. Place the white mouthpiece fully into your mouth and close your lips around it. Make sure that the SYMBICORT inhaler is upright and that the opening of the mouthpiece is pointing towards the back of your throat (see Figure 5).

8. Breathe in (inhale) deeply and slowly through your mouth. Press down firmly and fully on the top of the counter on the SYMBICORT inhaler to release the medicine (see Figures 3 and 4).
9. Continue to breathe in (inhale) and hold your breath for about 10 seconds, or for as long as is comfortable. Before you breathe out (exhale), release your finger from the top of the counter. Keep the SYMBICORT inhaler upright and remove from your mouth.
10. Shake the SYMBICORT inhaler again for 5 seconds and repeat steps 7 to 9.

After using your SYMBICORT inhaler

11. After use, close the mouthpiece cover by pushing until it clicks in place.
12. After you finish taking SYMBICORT (2 puffs), rinse your mouth with water. Spit out the water. Do not swallow it.

Reading the counter

- The arrow on the counter on the top of the SYMBICORT inhaler points to the number of inhalations (puffs) left in your inhaler.

COUNTER

- The counter will count down each time you release a puff of medicine (either when priming your SYMBICORT inhaler or when taking the medicine).
- When the arrow on the counter approaches 20, you will notice the beginning of a yellow area letting you know that it is time to call your healthcare provider for a refill.

COUNTER

- It is important that you pay attention to the number of inhalations (puffs) left in your SYMBICORT inhaler by reading the counter. Throw away SYMBICORT when the counter shows zero (“0”) or 3 months after you take your SYMBICORT inhaler out of its foil pouch, whichever comes first. Your SYMBICORT inhaler may not feel empty and it may continue to operate, but you will not get the right amount of medicine if you keep using it. Use a new SYMBICORT inhaler and follow the instructions for priming (see instruction 5 above).

How to clean your SYMBICORT inhaler

Clean the white mouthpiece of your SYMBICORT inhaler every 7 days. To clean the mouthpiece:

- Remove the grey mouthpiece cover
- Wipe the inside and outside of the white mouthpiece opening with a clean, dry cloth
- Replace the mouthpiece cover
- Do not put the SYMBICORT inhaler into water
- Do not try to take apart your SYMBICORT inhaler

Manufactured for: AstraZeneca Pharmaceuticals LP, Wilmington, DE 19850

By: AstraZeneca Dunkerque Production, Dunkerque, France

Product of France

This Patient Information and Instructions for Use has been approved by the U.S. Food and Drug Administration.

SYMBICORT is a trademark of the AstraZeneca group of companies. FORADIL AEROLIZER is a trademark of Novartis Pharmaceuticals Corporation.

©AstraZeneca 2017

Revised: December 2017

Medication Guide

SYMBICORT (SIM-bi-kort)
(budesonide 80 mcg and formoterol fumarate dihydrate 4.5 mcg)

Inhalation Aerosol

SYMBICORT (SIM-bi-kort)
(budesonide 160 mcg and formoterol fumarate dihydrate 4.5 mcg)

Inhalation Aerosol

What is the most important information I should know about SYMBICORT?

SYMBICORT can cause serious side effects, including:

1. People with asthma who take long-acting beta2-adrenergic agonist (LABA) medicines such as formoterol (one of the medicines in SYMBICORT) have an increased risk of death from asthma problems. It is not known whether budesonide, the other medicine in SYMBICORT, reduces the risk of death from asthma problems seen with formoterol.
Call your healthcare provider if breathing problems worsen over time while using SYMBICORT. You may need different treatment.
Get emergency medical care if:
  1. your breathing problems worsen quickly.
  2. you use your rescue inhaler medicine, but it does not relieve your breathing problems.
2. SYMBICORT should be used only if your healthcare provider decides that your asthma is not well controlled with a long-term asthma-control medicine, such as an inhaled corticosteroid.
3. When your asthma is well controlled, your healthcare provider may tell you to stop taking SYMBICORT. Your healthcare provider will decide if you can stop SYMBICORT without loss of asthma control. Your healthcare provider may prescribe a different long-term asthma-control medicine for you, such as an inhaled corticosteroid.
4. Children and adolescents who take LABA medicines may have an increased risk of being hospitalized for asthma problems.

What is SYMBICORT?

SYMBICORT combines an inhaled corticosteroid medicine, budesonide and a LABA medicine, formoterol.

- Inhaled corticosteroids help to decrease inflammation in the lungs. Inflammation in the lungs can lead to breathing problems.
- LABA medicines are used in people with chronic obstructive pulmonary disease (COPD) and asthma. LABA medicines help the muscles around the airways in your lungs stay relaxed to prevent symptoms such as wheezing, cough, chest tightness, and shortness of breath. These symptoms can happen when the muscles around the airways tighten. This makes it hard to breathe. In severe cases, wheezing can stop your breathing and may lead to death if not treated right away.

SYMBICORT is used for asthma and COPD as follows:

- Asthma: SYMBICORT is used to control symptoms of asthma, and prevent symptoms such as wheezing in adults and children ages 6 and older.
SYMBICORT contains formoterol. LABA medicines such as formoterol increase the risk of death from asthma problems. SYMBICORT is not for adults and children with asthma who are well controlled with an asthma-control medicine such as a low to medium dose of an inhaled corticosteroid medicine.
SYMBICORT is not used to relieve sudden breathing problems.
It is not known if SYMBICORT is safe and effective in children less than 6 years of age with asthma.
- COPD: COPD is a long-term (chronic) lung disease that includes chronic bronchitis, emphysema, or both. SYMBICORT 160/4.5 mcg is used long-term, as 2 inhalations 2 times each day, to improve symptoms of COPD for better breathing and to reduce the number of flare-ups (the worsening of your COPD symptoms for several days).
SYMBICORT is not used to relieve sudden breathing problems.

Do not use SYMBICORT:

- to treat sudden severe symptoms of asthma or COPD.
- if you are allergic to any of the ingredients in SYMBICORT. See the end of the Medication Guide for a list of ingredients in SYMBICORT.

Before you use SYMBICORT, tell your healthcare provider about all of your medical conditions, including if you:

- have heart problems.
- have high blood pressure.
- have seizures.
- have thyroid problems.
- have diabetes.
- have liver problems.
- have osteoporosis.
- have an immune system problem.
- have eye problems such as increased pressure in the eye, glaucoma, or cataracts.
- are allergic to any medicines.
- have any type of viral, bacterial, fungal, or parasitic infection.
- are exposed to chicken pox or measles.
- are pregnant or plan to become pregnant. It is not known if SYMBICORT may harm your unborn baby.
- are breastfeeding. Budesonide, one of the active ingredients in SYMBICORT, passes into breast milk. You and your healthcare provider should decide if you will take SYMBICORT while breast-feeding.

Tell your healthcare provider about all the medicines you take including prescription and over-the-counter medicines, vitamins, and herbal supplements. SYMBICORT and certain other medicines may interact with each other. This may cause serious side effects. Especially tell your healthcare provider if you take antifungal or anti-HIV medicines.

Know all the medicines you take. Keep a list and show it to your healthcare provider and pharmacist each time you get a new medicine.

How should I use SYMBICORT?

See the step-by-step instructions for using SYMBICORT at the end of this Medication Guide. Do not use SYMBICORT unless your healthcare provider has taught you and you understand everything. Ask your healthcare provider or pharmacist if you have any questions.

- Use SYMBICORT exactly as prescribed. Do not use SYMBICORT more often than prescribed. SYMBICORT comes in 2 strengths. Your healthcare provider has prescribed the strength that is best for you. Note the differences between SYMBICORT and your other inhaled medications, including the differences in prescribed use and physical appearance.
- Children should use SYMBICORT with an adult’s help, as instructed by the child’s healthcare provider.
- SYMBICORT should be taken every day as 2 puffs in the morning and 2 puffs in the evening about 12 hours apart.
- If you miss a dose of SYMBICORT, you should take your next dose at the same time you normally do.
- Rinse your mouth with water and spit the water out after each dose (2 puffs) of SYMBICORT. Do not swallow the water. This will help to lessen the chance of getting a fungus infection (thrush) in the mouth and throat.
- If you take too much SYMBICORT, call your healthcare provider or go to the nearest hospital emergency room right away if you have any unusual symptoms, such as worsening shortness of breath, chest pain, increased heart rate, or shakiness.
- Do not spray SYMBICORT in your eyes. If you accidentally get SYMBICORT in your eyes, rinse your eyes with water, and if redness or irritation persists, consult your healthcare provider.
- Do not change or stop any medicines used to control or treat your breathing problems. Your healthcare provider will change your medicines as needed.
- While you are using SYMBICORT 2 times each day, do not use other medicines that contain a LABA for any reason. Ask your healthcare provider or pharmacist if any of your other medicines are LABA medicines.
- SYMBICORT does not relieve sudden symptoms. Always have a rescue inhaler medicine with you to treat sudden symptoms. If you do not have a rescue inhaler, call your healthcare provider to have one prescribed for you.
- Call your healthcare provider or get medical care right away if:
  - your breathing problems worsen with SYMBICORT.
  - you need to use your rescue inhaler medicine more often than usual.
  - your rescue inhaler medicine does not work as well for you at relieving symptoms.
  - your peak flow meter results decrease. Your healthcare provider will tell you the numbers that are right for you.
  - your symptoms do not improve after using SYMBICORT regularly for 1 week.

What are the possible side effects of SYMBICORT?

SYMBICORT may cause serious side effects

- See “What is the most important information I should know about SYMBICORT?”
- Using too much of a LABA medicine may cause:

- chest pain
- a fast and irregular heartbeat
- tremor

- increased blood pressure
- headache
- nervousness

- Fungal infection in your mouth or throat (thrush). Rinse your mouth with water without swallowing after using SYMBICORT to help reduce your chance of getting thrush.
- Pneumonia and other lower respiratory tract infections. People with COPD have a higher chance of getting pneumonia and other lung infections. Inhaled corticosteroids may increase the chance of getting pneumonia. Call your healthcare provider if you notice any of these symptoms:

- increase in mucus (sputum) production
- fever
- increased cough

- change in mucus color
- chills
- increased breathing problems

- Immune system effects and a higher chance for infections. Tell your healthcare provider about any signs of infection such as:

- fever
- body aches
- feeling tired
- vomiting

- pain
- chills
- nausea

- Adrenal insufficiency. Adrenal insufficiency is a condition in which the adrenal glands do not make enough steroid hormones. This can happen when you stop taking oral corticosteroid medicines and start inhaled corticosteroid medicine.
- Increased wheezing right after taking SYMBICORT. Always have a rescue inhaler with you to treat sudden wheezing.
- Serious allergic reactions including rash, hives, swelling of the face, mouth, and tongue, and breathing problems. Call your healthcare provider or get emergency medical care if you get any symptoms of a serious allergic reaction.
- Lower bone mineral density. This can happen in people who have a high chance for low bone mineral density (osteoporosis). Your healthcare provider should check you for this during treatment with SYMBICORT.
- Slowed growth in children. A child’s growth should be checked regularly while using SYMBICORT.
- Eye problems including glaucoma and cataracts. You should have regular eye exams while using SYMBICORT.
- Swelling of your blood vessels. This can happen in people with asthma. Tell your healthcare provider right away if you have:

- a feeling of pins and needles or numbness of your arms or legs
- rash

- flu like symptoms
- pain and swelling of the sinuses

- Decreases in blood potassium levels (hypokalemia).
- Increases in blood sugar levels (hyperglycemia).

The most common side effects of SYMBICORT include:

People with asthma:

- throat irritation
- upper respiratory tract infection
- inflammation of mucous membranes of the sinuses (sinusitis)
- back pain
- stomach discomfort

- thrush in the mouth and throat
- headache
- throat pain
- flu
- nasal congestion
- vomiting

People with COPD:

- throat irritation
- thrush in the mouth and throat
- infection and inflammation of the mucous membranes of the bronchial tubes (bronchitis)
- inflammation of mucous membranes in the sinuses (sinusitis)
- upper respiratory tract infection

Tell your healthcare provider about any side effect that bothers you or that does not go away.

These are not all the possible side effects of SYMBICORT.

Call your doctor for medical advice about side effects. You may report side effects to FDA at 1-800-FDA-1088.

You may also report side effects to AstraZeneca at 1-800-236-9933.

How should I store SYMBICORT?

- Store SYMBICORT at room temperature between 68°F to 77°F (20°C to 25°C).
- Store SYMBICORT with the mouthpiece down.
- The contents of your SYMBICORT canister are under pressure. Do not puncture or throw the canister into a fire or incinerator. Do not use or store it near heat or open flame. Storage above 120ºF may cause the canister to burst.
- Throw away SYMBICORT when the counter reaches zero (“0”) or 3 months after you take SYMBICORT out of its foil pouch, whichever comes first.
- Keep SYMBICORT and all medicines out of the reach of children.

General Information about the safe and effective use of SYMBICORT.

Medicines are sometimes prescribed for purposes other than those listed in a Medication Guide. Do not use SYMBICORT for a condition for which it was not prescribed. Do not give SYMBICORT to other people, even if they have the same symptoms that you have. It may harm them.

You can ask your healthcare provider or pharmacist for information about SYMBICORT that is written for health professionals.

What are the ingredients in SYMBICORT?

Active ingredients: micronized budesonide and micronized formoterol fumarate dihydrate
Inactive ingredients: hydrofluroalkane (HFA 227), povidone K25 USP, and polyethylene glycol 1000 NF

Manufactured for: AstraZeneca Pharmaceuticals LP, Wilmington, DE 19850

By: AstraZeneca Dunkerque Production, Dunkerque, France Product of France

For more information, call 1-800-236-9933 or go to www.MySymbicort.com

Revised: September 2017